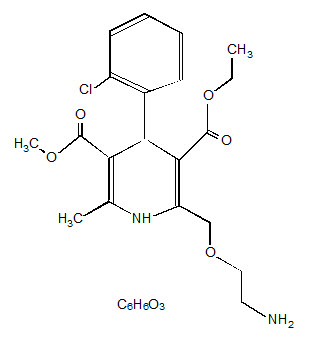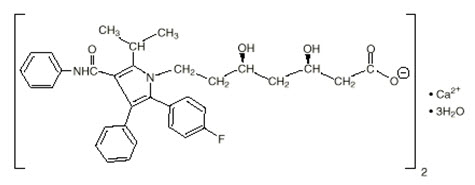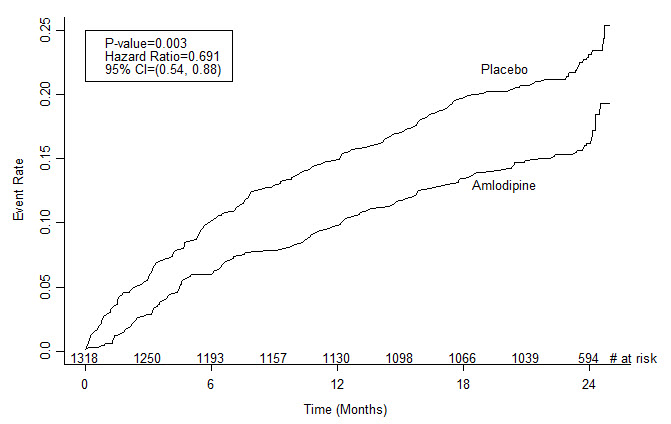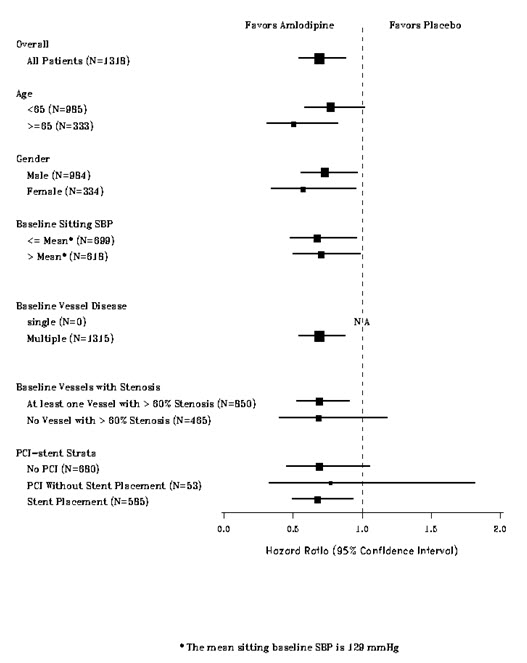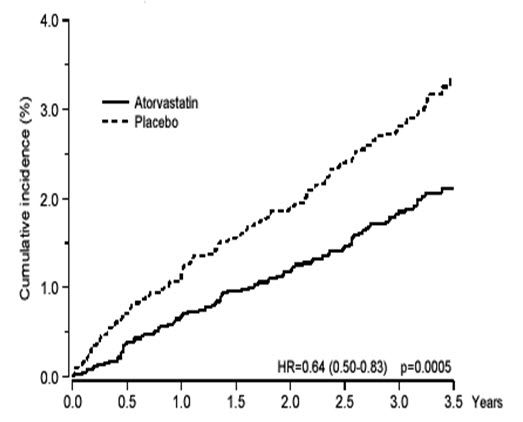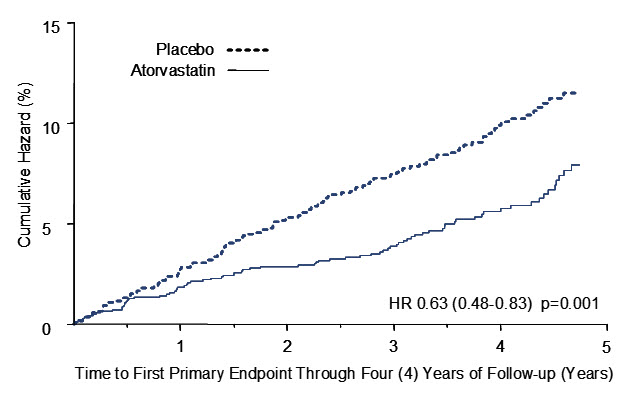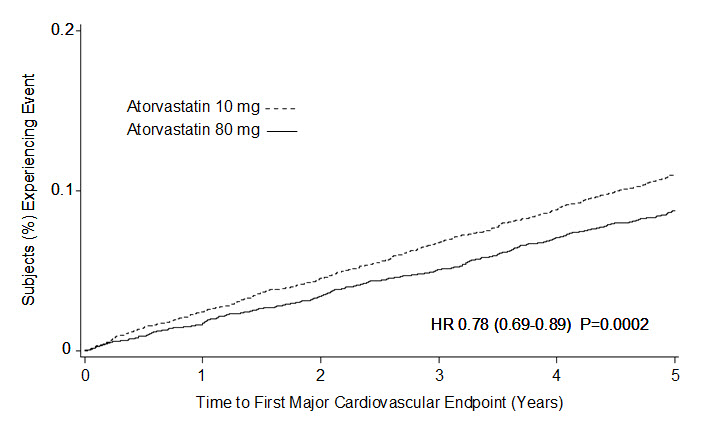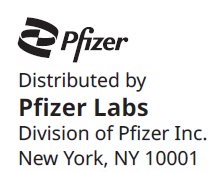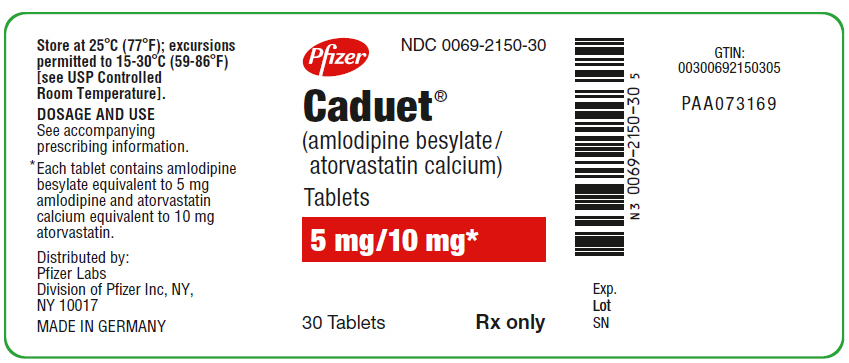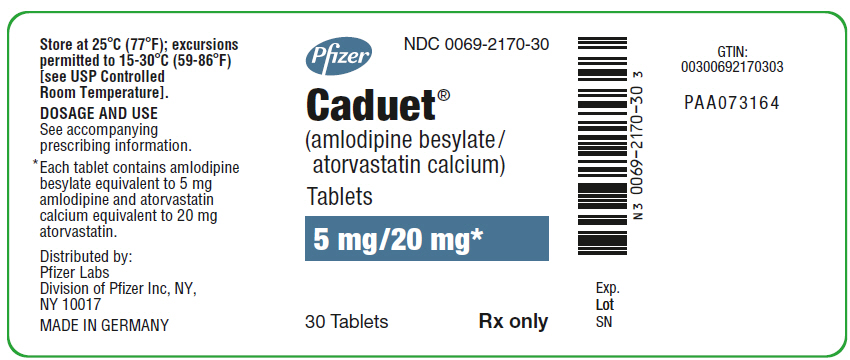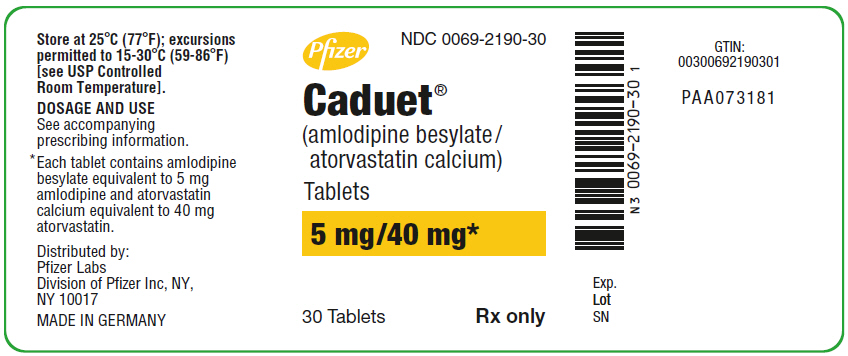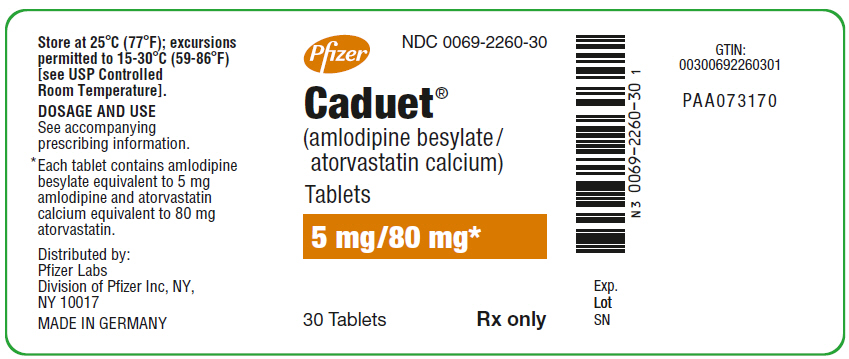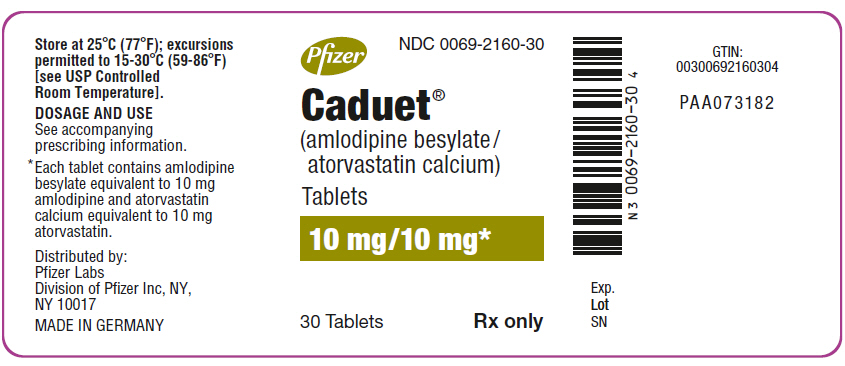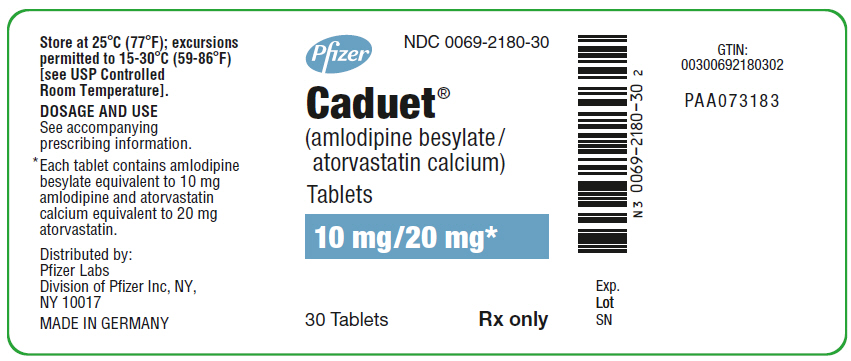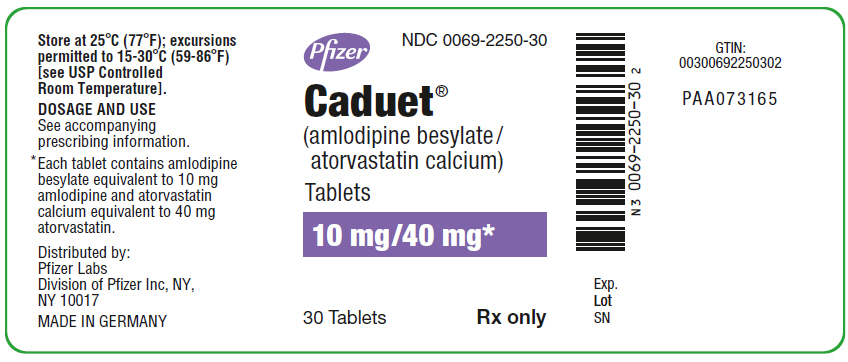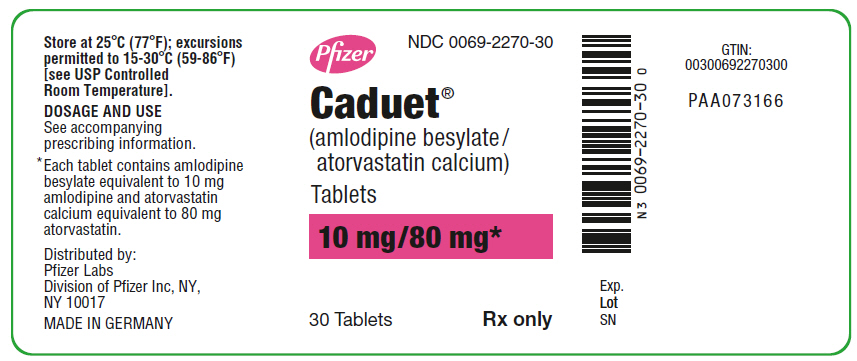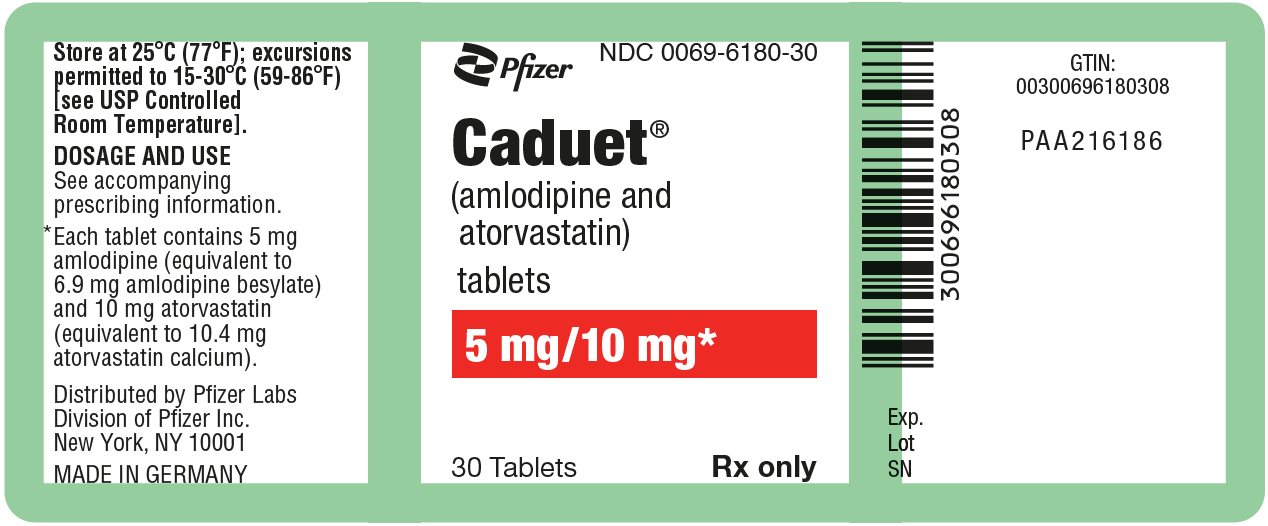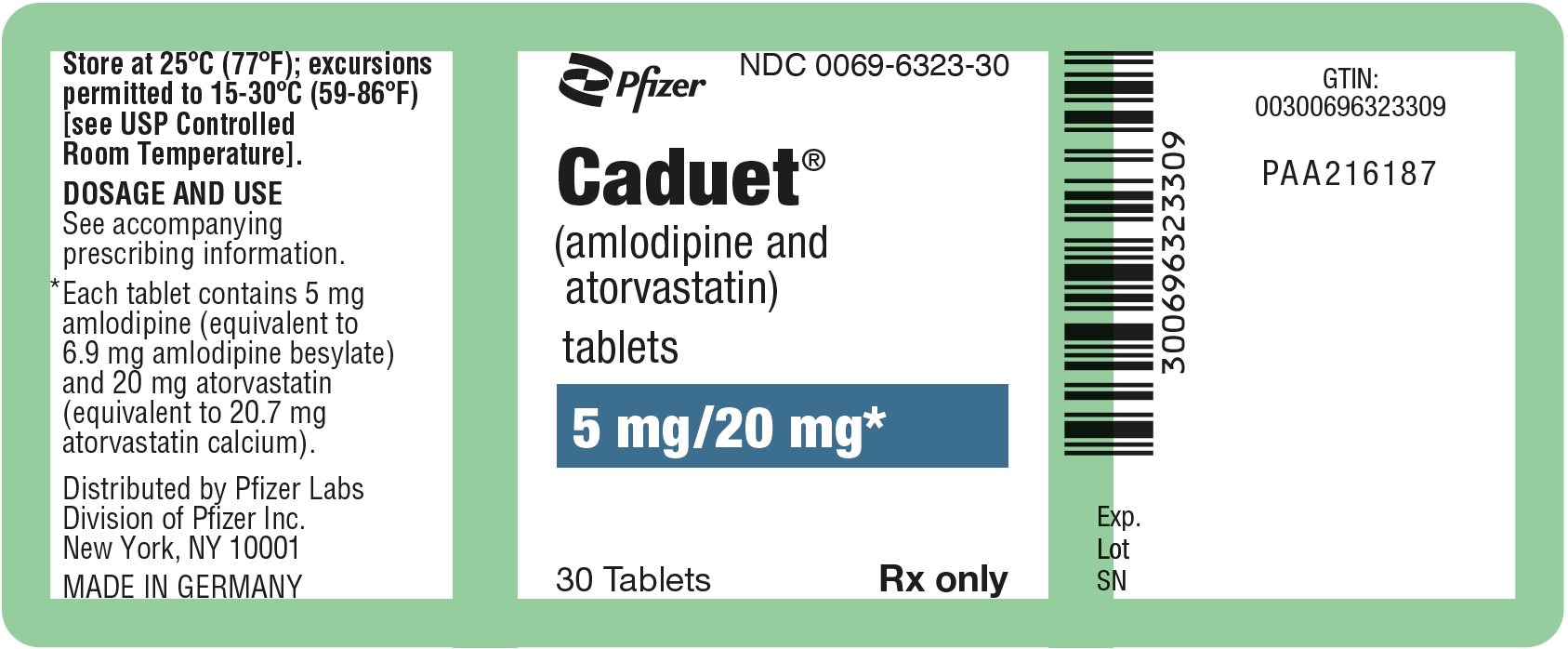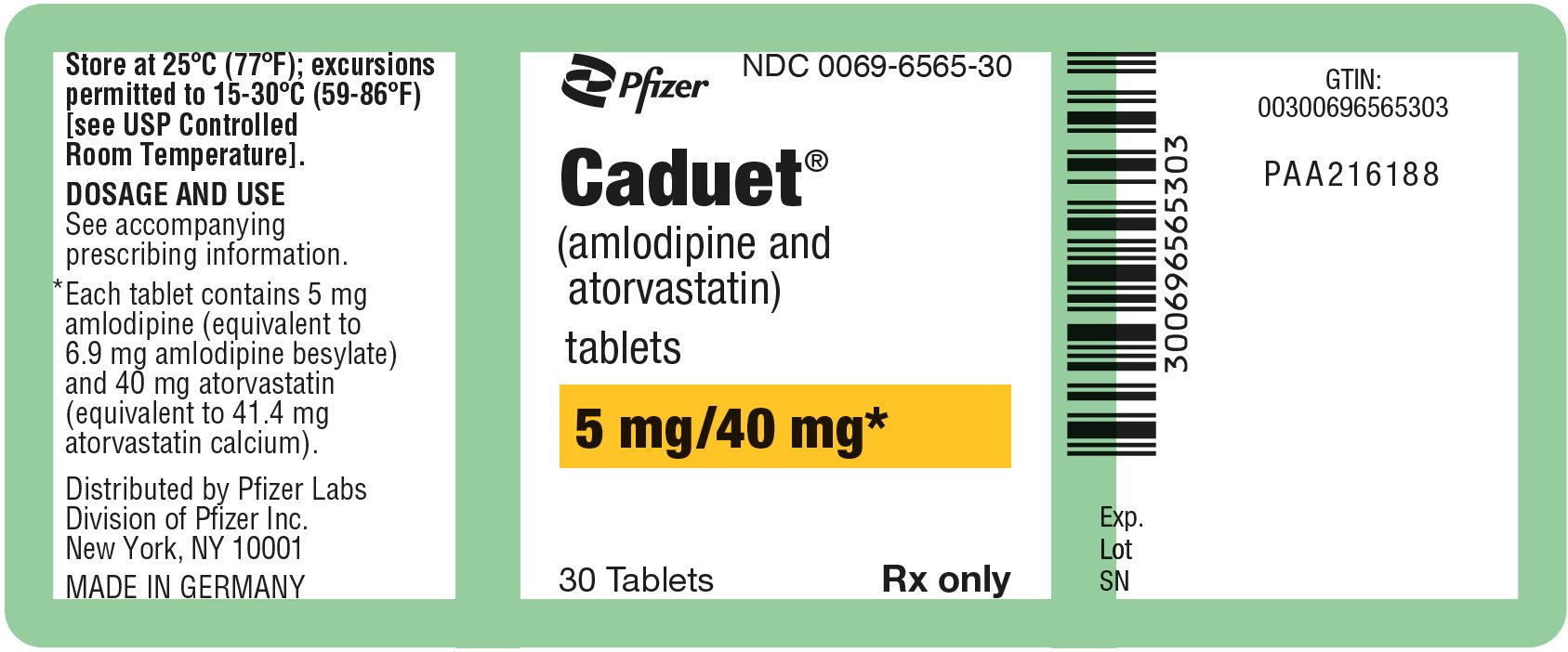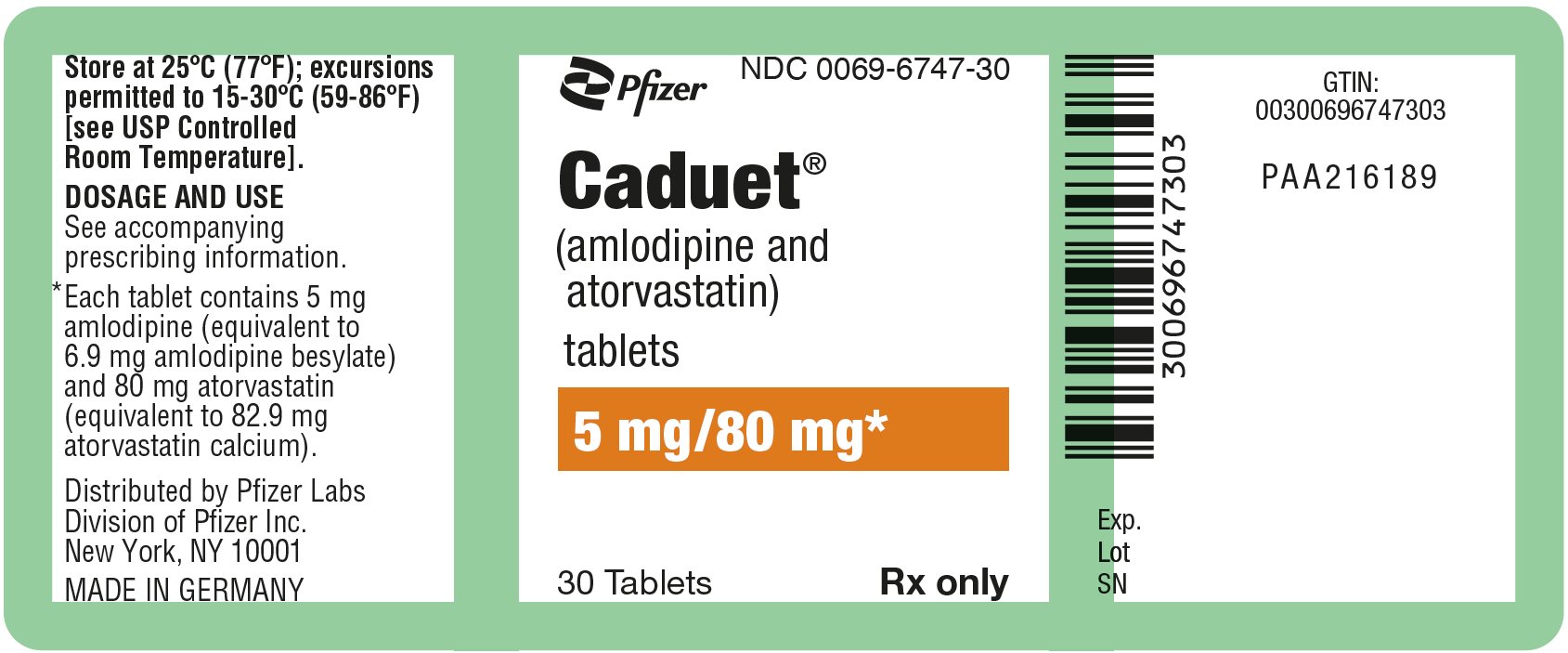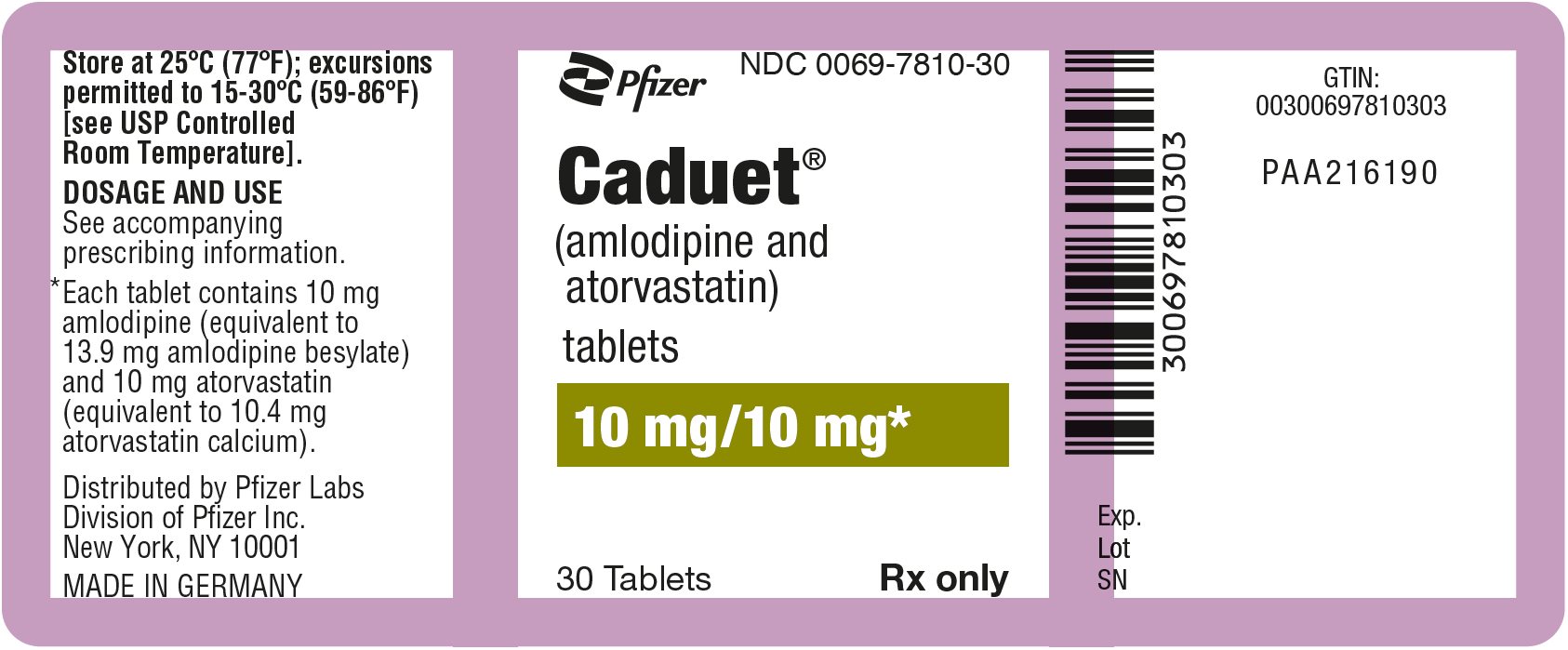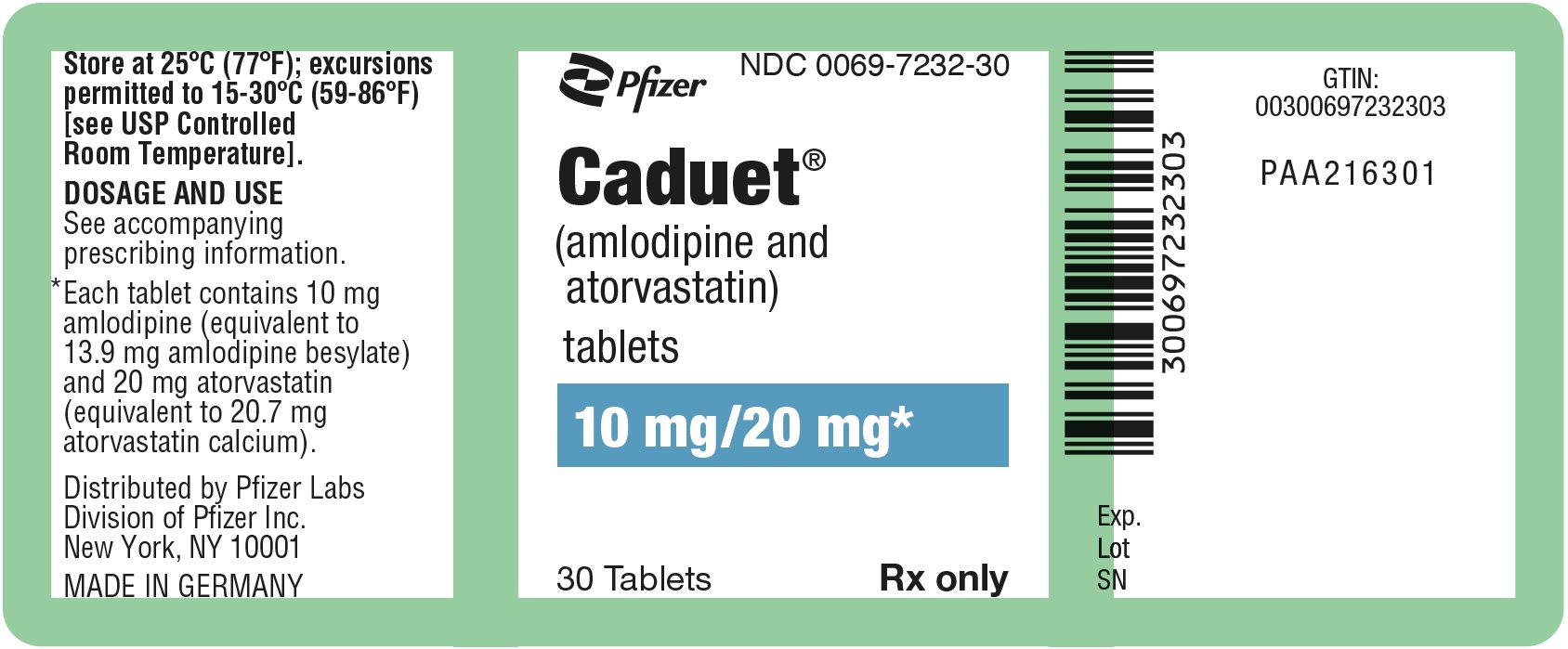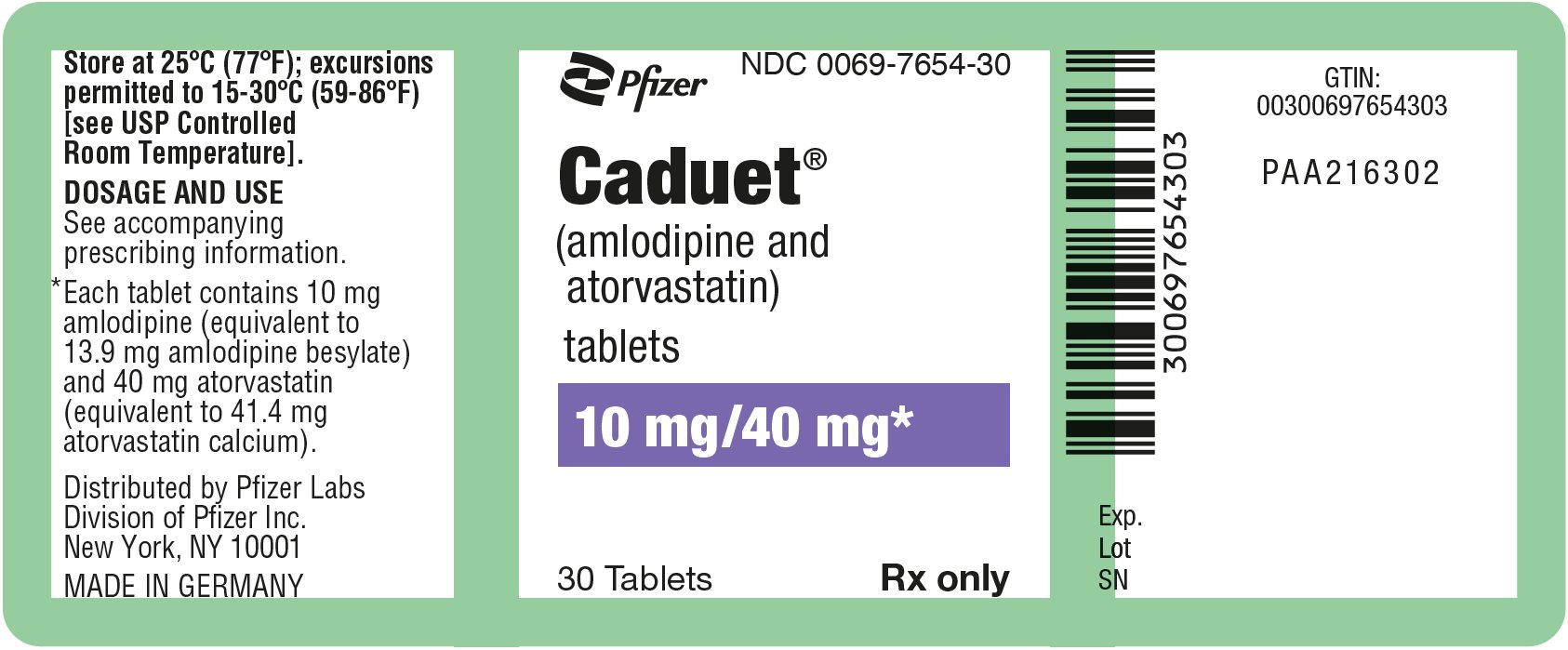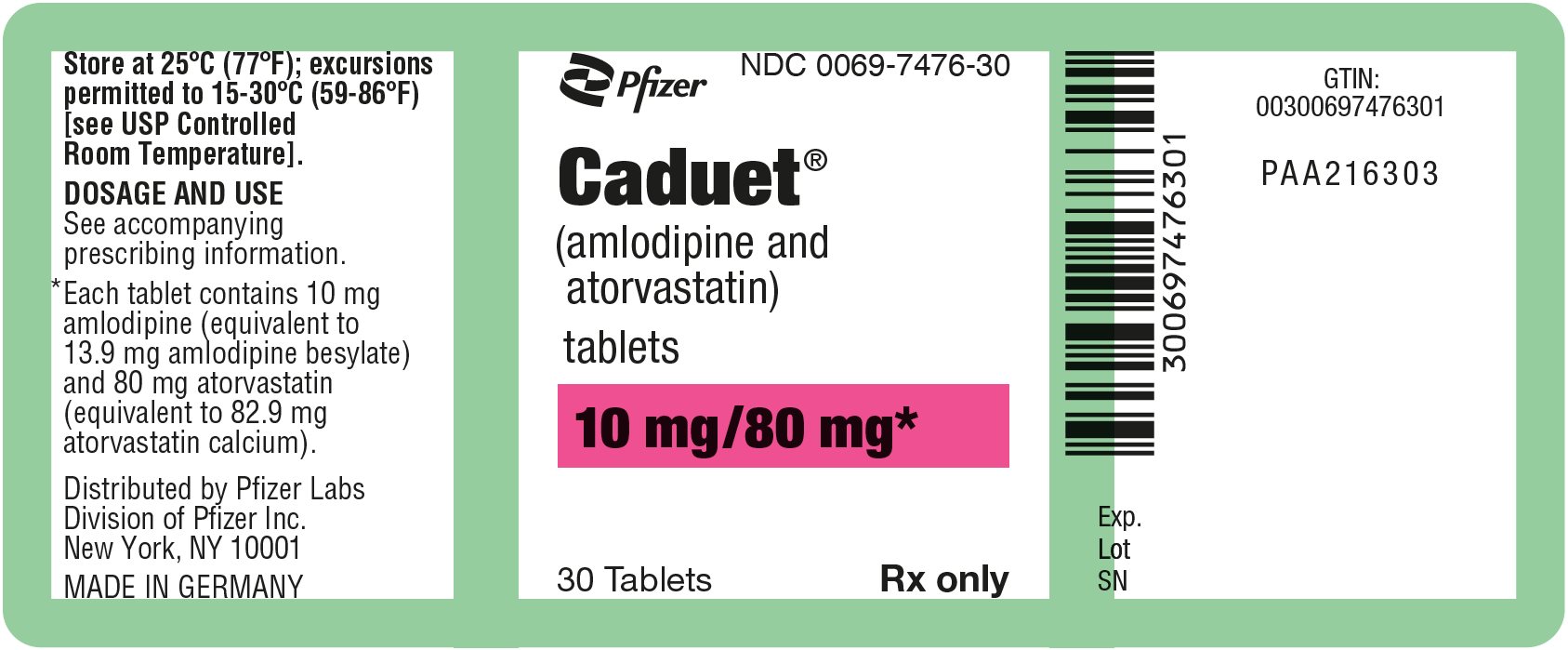 DRUG LABEL: Caduet
NDC: 0069-2150 | Form: TABLET, FILM COATED
Manufacturer: Pfizer Laboratories Div Pfizer Inc
Category: prescription | Type: HUMAN PRESCRIPTION DRUG LABEL
Date: 20250303

ACTIVE INGREDIENTS: AMLODIPINE BESYLATE 5 mg/1 1; ATORVASTATIN CALCIUM TRIHYDRATE 10 mg/1 1
INACTIVE INGREDIENTS: CALCIUM CARBONATE; CROSCARMELLOSE SODIUM; MICROCRYSTALLINE CELLULOSE; POLYSORBATE 80; HYDROXYPROPYL CELLULOSE (1600000 WAMW); WATER; SILICON DIOXIDE; MAGNESIUM STEARATE; POLYVINYL ALCOHOL, UNSPECIFIED; TITANIUM DIOXIDE; POLYETHYLENE GLYCOL 3000; TALC

HIGHLIGHTS OF PRESCRIBING INFORMATION

These highlights do not include all the information needed to use CADUET safely and effectively. See full prescribing information for CADUET.
CADUET® (amlodipine and atorvastatin) tablets, for oral use
Initial U.S. Approval: 2004

RECENT MAJOR CHANGES

Contraindications, Pregnancy and Lactation (4) | Removed 05/2024
Warnings and Precautions, CNS Toxicity (5.7) | Removed 05/2024

1 INDICATIONS AND USAGE

CADUET is a combination of amlodipine besylate, a calcium channel blocker, and atorvastatin calcium, a HMG-CoA-reductase inhibitor (statin), indicated in patients for whom treatment with both amlodipine and atorvastatin is appropriate (1).

Amlodipine is indicated for the treatment of hypertension, to lower blood pressure. Lowering blood pressure reduces the risk of fatal and non-fatal cardiovascular events, primarily strokes and myocardial infarctions.

Amlodipine is indicated for the treatment of Coronary Artery Disease (1).

Atorvastatin is indicated (1):

• To reduce the risk of:

- Myocardial infarction (MI), stroke, revascularization procedures, and angina in adults with multiple risk factors for coronary heart disease (CHD) but without clinically evident CHD.
- MI and stroke in adults with type 2 diabetes mellitus with multiple risk factors for CHD but without clinically evident CHD.
- Non-fatal MI, fatal and non-fatal stroke, revascularization procedures, hospitalization for congestive heart failure, and angina in adults with clinically evident CHD.

• As an adjunct to diet to reduce low-density lipoprotein (LDL-C) in:

- Adults with primary hyperlipidemia.
- Adults and pediatric patients aged 10 years and older with heterozygous familial hypercholesterolemia (HeFH).

• As an adjunct to other LDL-C-lowering therapies to reduce LDL-C in adults and pediatric patients aged 10 years and older with homozygous familial hypercholesterolemia.

• As an adjunct to diet for the treatment of adults with:

- Primary dysbetalipoproteinemia.
- Hypertriglyceridemia.

2 DOSAGE AND ADMINISTRATION

 | Usual starting dose (mg daily) | Maximum dose (mg daily)
Amlodipine | 5 [Start small adults or children, fragile, or elderly patients, or patients with hepatic insufficiency on 2.5 mg once daily (2).] | 10
Atorvastatin | 10–20 [Start patients requiring large LDL-C reduction (> 45%) at 40 mg once daily (2).] | 80

3 DOSAGE FORMS AND STRENGTHS

Tablets contain amlodipine besylate equivalent to amlodipine 5 or 10 mg and atorvastatin calcium equivalent to atorvastatin 10, 20, 40, or 80 mg (3).

4 CONTRAINDICATIONS

- Acute liver failure or decompensated cirrhosis (4).
- Hypersensitivity to amlodipine, atorvastatin or any excipient in CADUET (4).

5 WARNINGS AND PRECAUTIONS

• Myopathy and Rhabdomyolysis: Risk factors include age 65 years or greater, uncontrolled hypothyroidism, renal impairment, concomitant use with certain other drugs, and higher CADUET dosage. Discontinue CADUET if markedly elevated CK levels occur or myopathy is diagnosed or suspected. Temporarily discontinue CADUET in patients experiencing an acute or serious condition at high risk of developing renal failure secondary to rhabdomyolysis. Inform patients of the risk of myopathy and rhabdomyolysis when starting or increasing CADUET dosage. Instruct patients to promptly report unexplained muscle pain, tenderness, or weakness, particularly if accompanied by malaise or fever (2, 5.1, 7.3, 8.5, 8.6).

• Immune-Mediated Necrotizing Myopathy (IMNM): Rare reports of IMNM, an autoimmune myopathy, have been reported with statin use. Discontinue CADUET if IMNM is suspected (5.2).

• Hepatic Dysfunction: Increases in serum transaminases have occurred, some persistent. Rare reports of fatal and non-fatal hepatic failure have occurred. Consider testing liver enzymes before initiating therapy and as clinically indicated thereafter. If serious hepatic injury with clinical symptoms and/or hyperbilirubinemia or jaundice occurs, promptly discontinue CADUET (5.3).

• Angina or myocardial infarction may occur with initiation or dose increase (5.4)

• Symptomatic hypotension is possible, particularly in patients with severe aortic stenosis. However, acute hypotension is unlikely (5.5).

6 ADVERSE REACTIONS

Most common adverse reaction to amlodipine is edema which occurred in a dose related manner (6.1).

Most common adverse reactions (incidence ≥ 5%) are nasopharyngitis, arthralgia, diarrhea, pain in extremity, and urinary tract infection to atorvastatin (6.1).

To report SUSPECTED ADVERSE REACTIONS, contact Pfizer Inc. at 1-800-438-1985 or FDA at 1-800-FDA-1088 or www.fda.gov/medwatch

7 DRUG INTERACTIONS

- See full prescribing information for details regarding concomitant use of CADUET with other drugs or grapefruit juice that increase the risk of myopathy and rhabdomyolysis (2.5, 7.3).
- Rifampin: May reduce atorvastatin plasma concentrations. Administer simultaneously with atorvastatin (7.4).
- Oral Contraceptives: May increase plasma levels of norethindrone and ethinyl estradiol; consider this effect when selecting an oral contraceptive (7.5).
- Digoxin: May increase digoxin plasma levels; monitor patients appropriately (7.5).

8 USE IN SPECIFIC POPULATIONS

- Pregnancy: May cause fetal harm (8.1).
- Lactation: Breastfeeding not recommended during treatment with CADUET (8.2).

FULL PRESCRIBING INFORMATION

1 INDICATIONS AND USAGE

CADUET (amlodipine and atorvastatin) is indicated in patients for whom treatment with both amlodipine and atorvastatin is appropriate.

Amlodipine

Hypertension

Amlodipine is indicated for the treatment of hypertension, to lower blood pressure. Lowering blood pressure reduces the risk of fatal and non-fatal cardiovascular events, primarily strokes and myocardial infarctions. These benefits have been seen in controlled trials of antihypertensive drugs from a wide variety of pharmacologic classes including amlodipine.

Control of high blood pressure should be part of comprehensive cardiovascular risk management, including, as appropriate, lipid control, diabetes management, antithrombotic therapy, smoking cessation, exercise, and limited sodium intake. Many patients will require more than one drug to achieve blood pressure goals. For specific advice on goals and management, see published guidelines, such as those of the National High Blood Pressure Education Program’s Joint National Committee on Prevention, Detection, Evaluation, and Treatment of High Blood Pressure (JNC).

Numerous antihypertensive drugs, from a variety of pharmacologic classes and with different mechanisms of action, have been shown in randomized controlled trials to reduce cardiovascular morbidity and mortality, and it can be concluded that it is blood pressure reduction, and not some other pharmacologic property of the drugs, that is largely responsible for those benefits. The largest and most consistent cardiovascular outcome benefit has been a reduction in the risk of stroke, but reductions in myocardial infarction and cardiovascular mortality also have been seen regularly.

Elevated systolic or diastolic pressure causes increased cardiovascular risk, and the absolute risk increase per mmHg is greater at higher blood pressures, so that even modest reductions of severe hypertension can provide substantial benefit. Relative risk reduction from blood pressure reduction is similar across populations with varying absolute risk, so the absolute benefit is greater in patients who are at higher risk independent of their hypertension (for example, patients with diabetes or hyperlipidemia), and such patients would be expected to benefit from more aggressive treatment to a lower blood pressure goal.

Some antihypertensive drugs have smaller blood pressure effects (as monotherapy) in black patients, and many antihypertensive drugs have additional approved indications and effects (e.g., on angina, heart failure, or diabetic kidney disease). These considerations may guide selection of therapy.

Amlodipine may be used alone or in combination with other antihypertensive agents.

Coronary Artery Disease (CAD)

Chronic Stable Angina

Amlodipine is indicated for the symptomatic treatment of chronic stable angina. Amlodipine may be used alone or in combination with other antianginal agents.

Vasospastic Angina (Prinzmetal’s or Variant Angina)

Amlodipine is indicated for the treatment of confirmed or suspected vasospastic angina. Amlodipine may be used as monotherapy or in combination with other antianginal agents.

Angiographically Documented CAD

In patients with recently documented CAD by angiography and without heart failure or an ejection fraction < 40%, amlodipine is indicated to reduce the risk of hospitalization for angina and to reduce the risk of a coronary revascularization procedure.

Atorvastatin

Atorvastatin is indicated:

• To reduce the risk of:

- Myocardial infarction (MI), stroke, revascularization procedures, and angina in adults with multiple risk factors for coronary heart disease (CHD) but without clinically evident CHD
- MI and stroke in adults with type 2 diabetes mellitus with multiple risk factors for CHD but without clinically evident CHD
- Non-fatal MI, fatal and non-fatal stroke, revascularization procedures, hospitalization for congestive heart failure, and angina in adults with clinically evident CHD

• As an adjunct to diet to reduce low-density lipoprotein cholesterol (LDL-C) in:

- Adults with primary hyperlipidemia.
- Adults and pediatric patients aged 10 years and older with heterozygous familial hypercholesterolemia (HeFH).

• As an adjunct to other LDL-C-lowering therapies, or alone if such treatments are unavailable, to reduce LDL C in adults and pediatric patients aged 10 years and older with homozygous familial hypercholesterolemia (HoFH).

• As an adjunct to diet for the treatment of adults with:

- Primary dysbetalipoproteinemia
- Hypertriglyceridemia

2 DOSAGE AND ADMINISTRATION

CADUET

Dosage of CADUET must be individualized on the basis of both effectiveness and tolerance for each individual component in the treatment of hypertension/angina and hyperlipidemia. Select doses of amlodipine and atorvastatin independently.

CADUET may be substituted for its individually titrated components. Patients may be given the equivalent dose of CADUET or a dose of CADUET with increased amounts of amlodipine, atorvastatin, or both for additional antianginal effects, blood pressure lowering, or lipid-lowering effect.

CADUET may be used to provide additional therapy for patients already on one of its components. CADUET may be used to initiate treatment in patients with hyperlipidemia and either hypertension or angina.

Important Dosage Information

Take CADUET orally once daily at any time of the day, with or without food.

Amlodipine

The usual initial antihypertensive oral dosage of amlodipine is 5 mg once daily, and the maximum dose is 10 mg once daily.

Pediatric (age > 6 years), small adult, fragile, or elderly patients, or patients with hepatic insufficiency may be started on 2.5 mg once daily and this dose may be used when adding amlodipine to other antihypertensive therapy.

Adjust dosage according to blood pressure goals. In general, wait 7 to 14 days between titration steps. Titration may proceed more rapidly, however, if clinically warranted, provided the patient is assessed frequently.

Angina The recommended dosage of amlodipine for chronic stable or vasospastic angina is 5–10 mg, with the lower dose suggested in the elderly and in patients with hepatic insufficiency. Most patients will require 10 mg for adequate effect.

Coronary Artery Disease The recommended dosage range of amlodipine for patients with CAD is 5–10 mg once daily. In clinical studies, the majority of patients required 10 mg [see Clinical Studies (14.4)].

Pediatrics The effective antihypertensive oral dose of amlodipine in pediatric patients ages 6–17 years is 2.5 mg to 5 mg once daily. Doses in excess of 5 mg daily have not been studied in pediatric patients [see Clinical Pharmacology (12.3) and Clinical Studies (14.1)].

Atorvastatin

Assess LDL-C when clinically appropriate, as early as 4 weeks after initiating atorvastatin, and adjust the ‎dosage if ‎‎necessary.‎ ‎

Recommended Dosage in Adult Patients

The recommended starting dosage of atorvastatin is 10 mg to 20 mg once daily. The dosage range is 10 mg to 80 mg once daily. Patients who require reduction in LDL-C greater than 45% may be started at 40 mg once daily.

Recommended Dosage in Pediatric Patients 10 Years of Age and Older with HeFH

The recommended starting dosage of atorvastatin is 10 mg once daily. The dosage range is 10 mg to 20 mg once daily.

Recommended Dosage in Pediatric Patients 10 Years of Age and Older with HoFH

The recommended starting dosage of atorvastatin is 10 mg to 20 mg once daily. The dosage range is 10 mg to 80 mg once daily.

Dosage Modifications Due to Drug Interactions

Concomitant use of atorvastatin with the following drugs requires dosage modification of atorvastatin [see Warnings and Precautions (5.1) and Drug Interactions (7.1)].

Anti-Viral Medications

• In patients taking saquinavir plus ritonavir, darunavir plus ritonavir, fosamprenavir, fosamprenavir plus ritonavir, elbasvir plus grazoprevir or letermovir, do not exceed atorvastatin 20 mg once daily.

• In patients taking nelfinavir, do not exceed atorvastatin 40 mg once daily.

Select Azole Antifungals or Macrolide Antibiotics

• In patients taking clarithromycin or itraconazole, do not exceed atorvastatin 20 mg once daily.

For additional recommendations regarding concomitant use of atorvastatin with other anti-viral medications, azole antifungals or macrolide antibiotics, [see Drug Interactions (7.1)].

3 DOSAGE FORMS AND STRENGTHS

CADUET tablets are formulated for oral administration in the following strength combinations:

 |  | Atorvastatin (mg)
 |  | 10 | 20 | 40 | 80
Amlodipine (mg) | 5 | X | X | X | X
Amlodipine (mg) | 10 | X | X | X | X

Combinations of atorvastatin with 5 mg amlodipine are film-coated white tablets and combinations of atorvastatin with 10 mg amlodipine are film-coated blue tablets.

4 CONTRAINDICATIONS

- Acute liver failure or decompensated cirrhosis [see Warnings and Precautions (5.3)].
- Hypersensitivity to amlodipine, atorvastatin or any excipients in ‎CADUET. Hypersensitivity reactions, including anaphylaxis, angioneurotic edema, erythema multiforme, Stevens-Johnson syndrome, and toxic epidermal necrolysis, have been reported [see Adverse Reactions (6.2)].

5 WARNINGS AND PRECAUTIONS

5.1 Myopathy and Rhabdomyolysis

CADUET may cause myopathy (muscle pain, tenderness, or weakness associated with elevated creatine kinase [CK]) and rhabdomyolysis. Acute kidney injury secondary to myoglobinuria and rare fatalities have occurred as a result of rhabdomyolysis in patients treated with statins, including CADUET.

Risk Factors for Myopathy

Risk factors for myopathy include age 65 years or greater, uncontrolled hypothyroidism, renal impairment, concomitant use with certain other drugs (including other lipid-lowering therapies), and higher CADUET dosage [see Drug Interactions (7.3) and Use in Specific Populations (8.5, 8.6)].

Steps to Prevent or Reduce the Risk of Myopathy and Rhabdomyolysis

CADUET exposure may be increased by drug interactions due to inhibition of cytochrome P450 enzyme 3A4 (CYP3A4) and/or transporters (e.g., breast cancer resistant protein [BCRP], organic anion-transporting polypeptide [OATP1B1/OATP1B3] and P-glycoprotein [P-gp]), resulting in an increased risk of myopathy and rhabdomyolysis. Concomitant use of cyclosporine, gemfibrozil, tipranavir plus ritonavir or glecaprevir plus pibrentasvir with CADUET is not recommended. CADUET dosage modifications are recommended for patients taking certain anti-viral, azole antifungals, or macrolide antibiotic medications [see Dosage and Administration (2)]. Cases of myopathy/rhabdomyolysis have been reported with atorvastatin co-administered with lipid modifying doses (> 1 gram/day) of niacin, fibrates, colchicine, and ledipasvir plus sofosbuvir [see Adverse Reactions (6.1)]. Consider if the benefit of use of these products outweighs the increased risk of myopathy and rhabdomyolysis [see Drug Interactions (7.3)].

Concomitant intake of large quantities, more than 1.2 liters daily, of grapefruit juice is not recommended in patients taking CADUET [see Drug Interactions (7.3)].

Discontinue CADUET if markedly elevated CK levels occur or if myopathy is either diagnosed or suspected. Muscle symptoms and CK elevations may resolve if CADUET is discontinued. Temporarily discontinue CADUET in patients experiencing an acute or serious condition at high risk of developing renal failure secondary to rhabdomyolysis (e.g., sepsis; shock; severe hypovolemia; major surgery; trauma; severe metabolic, endocrine, or electrolyte disorders; or uncontrolled epilepsy).

Inform patients of the risk of myopathy and rhabdomyolysis when starting or increasing the CADUET dosage. Instruct patients to promptly report any unexplained muscle pain, tenderness or weakness, particularly if accompanied by malaise or fever.

5.2 Immune-Mediated Necrotizing Myopathy

There have been rare reports of immune-mediated necrotizing myopathy (IMNM), an autoimmune myopathy, associated with statin use, including reports of recurrence when the same or a different statin was administered. IMNM is characterized by: proximal muscle weakness and elevated serum creatine kinase that persists despite discontinuation of statin treatment; positive anti-HMG-CoA reductase antibody; muscle biopsy showing necrotizing myopathy; and improvement with immunosuppressive agents. Additional neuromuscular and serologic testing may be necessary. Treatment with immunosuppressive agents may be required. Discontinue CADUET if IMNM is suspected.

5.3 Hepatic Dysfunction

Increases in serum transaminases have been reported with use of atorvastatin [see Adverse Reactions (6.1)]. In most cases, these changes appeared soon after initiation, were transient, were not accompanied by symptoms, and resolved or improved on continued therapy or after a brief interruption in therapy. Persistent increases to more than three times the ULN in serum transaminases have occurred in approximately 0.7% of patients receiving atorvastatin in clinical trials. There have been rare postmarketing reports of fatal and non-fatal hepatic failure in patients taking statins, including atorvastatin.

Patients who consume substantial quantities of alcohol and/or have a history of liver disease may be at increased risk for hepatic injury [see Use in Specific Populations (8.7)].

Consider liver enzyme testing before atorvastatin initiation and when clinically indicated thereafter. Atorvastatin is contraindicated in patients with acute liver failure or decompensated cirrhosis [see Contraindications (4)]. If serious hepatic injury with clinical symptoms and/or hyperbilirubinemia or jaundice occurs, promptly discontinue atorvastatin.

5.4 Increased Angina and Myocardial Infarction

Worsening angina and acute myocardial infarction can develop after starting or increasing the dose of amlodipine, particularly in patients with severe obstructive coronary artery disease.

5.5 Hypotension

Symptomatic hypotension is possible with use of amlodipine, particularly in patients with severe aortic stenosis. Because of the gradual onset of action, acute hypotension is unlikely.

5.6 Increases in HbA1c and Fasting Serum Glucose Levels

Increases in HbA1c and fasting serum glucose levels have been reported with statins, including atorvastatin. Optimize lifestyle measures, including regular exercise, maintaining a healthy body weight, and making healthy food choices.

5.7 Increased Risk of Hemorrhagic Stroke in Patients on Atorvastatin 80 mg with Recent Hemorrhagic Stroke

In a post-hoc analysis of the Stroke Prevention by Aggressive Reduction in Cholesterol Levels (SPARCL) trial where 2365 adult patients, without CHD who had a stroke or Transient Ischemic Attack (TIA) within the preceding 6 months, were treated with atorvastatin 80 mg, a higher incidence of hemorrhagic stroke was seen in the atorvastatin 80 mg group compared to placebo (55, 2.3% atorvastatin vs. 33, 1.4% placebo; HR: 1.68, 95% CI: 1.09, 2.59; p=0.0168). The incidence of fatal hemorrhagic stroke was similar across treatment groups (17 vs. 18 for the atorvastatin and placebo groups, respectively). The incidence of non-fatal hemorrhagic stroke was significantly higher in the atorvastatin group (38, 1.6%) as compared to the placebo group (16, 0.7%). Some baseline characteristics, including hemorrhagic and lacunar stroke on study entry, were associated with a higher incidence of hemorrhagic stroke in the atorvastatin group [see Adverse Reactions (6.1)]. Consider the risk/benefit of use of atorvastatin 80 mg in patients with recent hemorrhagic stroke.

6 ADVERSE REACTIONS

The following important adverse reactions are described below and elsewhere in the labeling:

• Myopathy and Rhabdomyolysis [see Warnings and Precautions (5.1)]

• Immune-Mediated Necrotizing Myopathy [see Warnings and Precautions (5.2)]

• Hepatic Dysfunction [see Warnings and Precautions (5.3)]

• Increases in HbA1c and Fasting Serum Glucose Levels [see Warnings and Precautions (5.6)]

6.1 Clinical Trials Experience

Because clinical trials are conducted under widely varying conditions,the adverse reaction rates observed in the clinical trials of a drug cannot be directly compared to rates in the clinical trials of another drug and may not reflect the rates observed in practice.

CADUET

CADUET (amlodipine/atorvastatin) has been evaluated for safety in 1092 patients in double-blind placebo-controlled studies treated for co-morbid hypertension and dyslipidemia. In general, treatment with CADUET was well tolerated. For the most part, adverse reactions have been mild or moderate in severity. In clinical trials with CADUET, no adverse reactions peculiar to this combination have been observed. Adverse reactions are similar in terms of nature, severity, and frequency to those reported previously with amlodipine and atorvastatin.

The following information is based on the clinical experience with amlodipine and atorvastatin.

Amlodipine

Amlodipine has been evaluated for safety in more than 11,000 patients in U.S. and foreign clinical trials. In general, treatment with amlodipine was well tolerated at doses up to 10 mg daily. Most adverse reactions reported during therapy with amlodipine were of mild or moderate severity. In controlled clinical trials directly comparing amlodipine (N=1730) at doses up to 10 mg to placebo (N=1250), discontinuation of amlodipine because of adverse reactions was required in only about 1.5% of patients and was not significantly different from placebo (about 1%). The most commonly reported side effects more frequent than placebo are dizziness and edema. The incidence (%) of side effects that occurred in a dose related manner are as follows:

 | Amlodipine
 | 2.5 mg | 5 mg | 10 mg | Placebo
 | N=275 | N=296 | N=268 | N=520
Edema | 1.8 | 3.0 | 10.8 | 0.6
Dizziness | 1.1 | 3.4 | 3.4 | 1.5
Flushing | 0.7 | 1.4 | 2.6 | 0.0
Palpitations | 0.7 | 1.4 | 4.5 | 0.6

Other adverse reactions that were not clearly dose related but were reported at an incidence greater than 1.0% in placebo-controlled clinical trials include the following:

 | Amlodipine (%) | Placebo (%)
 | (N=1730) | (N=1250)
Fatigue | 4.5 | 2.8
Nausea | 2.9 | 1.9
Abdominal Pain | 1.6 | 0.3
Somnolence | 1.4 | 0.6

Edema, flushing, palpitations, and somnolence appear to be more common in women than in men.

The following events occurred in < 1% but > 0.1% of patients treated with amlodipine in controlled clinical trials or under conditions of open trials or marketing experience where a causal relationship is uncertain; they are listed to alert the physician to a possible relationship:

Cardiovascular: arrhythmia (including ventricular tachycardia and atrial fibrillation), bradycardia, chest pain, peripheral ischemia, syncope, tachycardia, vasculitis.

Central and Peripheral Nervous System: hypoesthesia, neuropathy peripheral, paresthesia, tremor, vertigo.

Gastrointestinal: anorexia, constipation, dysphagia, diarrhea, flatulence, pancreatitis, vomiting, gingival hyperplasia.

General: allergic reaction, asthenia,2 back pain, hot flushes, malaise, pain, rigors, weight gain, weight decrease.

Musculoskeletal System: arthralgia, arthrosis, muscle cramps,2 myalgia.

Psychiatric: sexual dysfunction (male2 and female), insomnia, nervousness, depression, abnormal dreams, anxiety, depersonalization.

Respiratory System: dyspnea,2 epistaxis.

Skin and Appendages: angioedema, erythema multiforme, pruritus,2 rash,2 rash erythematous, rash maculopapular.

Special Senses: abnormal vision, conjunctivitis, diplopia, eye pain, tinnitus.

Urinary System: micturition frequency, micturition disorder, nocturia.

Autonomic Nervous System: dry mouth, sweating increased.

Metabolic and Nutritional: hyperglycemia, thirst.

Hemopoietic: leukopenia, purpura, thrombocytopenia.

^2 These events occurred in less than 1% in placebo controlled trials, but the incidence of these side effects was between 1% and 2% in all multiple dose studies.

Amlodipine therapy has not been associated with clinically significant changes in routine laboratory tests. No clinically relevant changes were noted in serum potassium, serum glucose, total TG, TC, HDL-C, uric acid, blood urea nitrogen, or creatinine.

Atorvastatin

In the atorvastatin placebo-controlled clinical trial database of 16066 patients (8755 atorvastatin vs. 7311 placebo; age range 10‑93 years, 39% female, 91% White, 3% Black or African American, 2% Asian, 4% other) with a median treatment duration of 53 weeks, the most common adverse reactions in patients treated with atorvastatin that led to treatment discontinuation and occurred at a rate greater than placebo were: myalgia (0.7%), diarrhea (0.5%), nausea (0.4%), alanine aminotransferase increase (0.4%), and hepatic enzyme increase (0.4%).

Table 2 summarizes adverse reactions, reported in ≥ 2% and at a rate greater than placebo in patients treated with atorvastatin (n=8755), from seventeen placebo-controlled trials.

Table 2. Adverse Reactions Occurring in ≥ 2% in Patients Atorvastatin-Treated with any Dose and Greater than Placebo

Adverse Reaction | % Placebo N=7311 | % 10 mg N=3908 | % 20 mg N=188 | % 40 mg N=604 | % 80 mg N=4055 | % Any dose N=8755
Nasopharyngitis | 8.2 | 12.9 | 5.3 | 7.0 | 4.2 | 8.3
Arthralgia | 6.5 | 8.9 | 11.7 | 10.6 | 4.3 | 6.9
Diarrhea | 6.3 | 7.3 | 6.4 | 14.1 | 5.2 | 6.8
Pain in extremity | 5.9 | 8.5 | 3.7 | 9.3 | 3.1 | 6.0
Urinary tract infection | 5.6 | 6.9 | 6.4 | 8.0 | 4.1 | 5.7
Dyspepsia | 4.3 | 5.9 | 3.2 | 6.0 | 3.3 | 4.7
Nausea | 3.5 | 3.7 | 3.7 | 7.1 | 3.8 | 4.0
Musculoskeletal pain | 3.6 | 5.2 | 3.2 | 5.1 | 2.3 | 3.8
Muscle spasms | 3.0 | 4.6 | 4.8 | 5.1 | 2.4 | 3.6
Myalgia | 3.1 | 3.6 | 5.9 | 8.4 | 2.7 | 3.5
Insomnia | 2.9 | 2.8 | 1.1 | 5.3 | 2.8 | 3.0
Pharyngolaryngeal pain | 2.1 | 3.9 | 1.6 | 2.8 | 0.7 | 2.3

Other adverse reactions reported in placebo-controlled trials include:

Body as a Whole: malaise, pyrexia

Digestive System: abdominal discomfort, eructation, flatulence, hepatitis, cholestasis

Musculoskeletal System: musculoskeletal pain, muscle fatigue, neck pain, joint swelling

Metabolic and Nutritional System: transaminases increase, liver function test abnormal, blood alkaline phosphatase increase, creatine phosphokinase increase, hyperglycemia

Nervous System: nightmare

Respiratory System: epistaxis

Skin and Appendages: urticaria

Special Senses: vision blurred, tinnitus

Urogenital System: white blood cells urine positive.

Elevations in Liver Enzyme Tests

Persistent elevations in serum transaminases, defined as more than 3 times the ULN and occurring on 2 or more occasions, occurred in 0.7% of patients who received atorvastatin in clinical trials. The incidence of these abnormalities was 0.2%, 0.2%, 0.6%, and 2.3% for 10, 20, 40, and 80 mg, respectively.

One patient in clinical trials developed jaundice. Increases in liver enzyme tests in other patients were not associated with jaundice or other clinical signs or symptoms. Upon dose reduction, drug interruption, or discontinuation, transaminase levels returned to or near pretreatment levels without sequelae. Eighteen of 30 patients with persistent liver enzyme elevations continued treatment with a reduced dose of atorvastatin.

Treating to New Targets Study (TNT)

In TNT, [see Clinical Studies (14.6)] 10,001 patients (age range 29–78 years, 19% female; 94% White, 3% Black or African American, 1% Asian, 2% other) with clinically evident CHD were treated with atorvastatin 10 mg daily (n=5006) or atorvastatin 80 mg daily (n=4995). In the high-dose atorvastatin group, there were more patients with serious adverse reactions (1.8%) and discontinuations due to adverse reactions (9.9%) as compared to the low-dose group (1.4%; 8.1%, respectively) during a median follow-up of 4.9 years. Persistent transaminase elevations (≥ 3 x ULN twice within 4–10 days) occurred in 1.3% of individuals with atorvastatin 80 mg and in 0.2% of individuals with atorvastatin 10 mg. Elevations of CK (≥ 10 x ULN) were higher in the high-dose atorvastatin group (0.3%) compared to the low-dose atorvastatin group (0.1%).

Stroke Prevention by Aggressive Reduction in Cholesterol Levels (SPARCL)

In SPARCL, 4731 patients (age range 21–92 years, 40% female; 93% White, 3% Black or African American, 1% Asian, 3% other) without clinically evident CHD but with a stroke or transient ischemic attack (TIA) within the previous 6 months were treated with atorvastatin 80 mg (n=2365) or placebo (n=2366) for a median follow-up of 4.9 years. There was a higher incidence of persistent hepatic transaminase elevations (≥ 3 x ULN twice within 4–10 days) in the atorvastatin group (0.9%) compared to placebo (0.1%). Elevations of CK (> 10 x ULN) were rare, but were higher in the atorvastatin group (0.1%) compared to placebo (0.0%). Diabetes was reported as an adverse reaction in 6.1% of subjects in the atorvastatin group and 3.8% of subjects in the placebo group.

In a post-hoc analysis, atorvastatin 80 mg reduced the incidence of ischemic stroke (9.2% vs. 11.6%) and increased the incidence of hemorrhagic stroke (2.3% vs. 1.4%) compared to placebo. The incidence of fatal hemorrhagic stroke was similar between groups (17 atorvastatin vs. 18 placebo). The incidence of non-fatal hemorrhagic strokes was significantly greater in the atorvastatin group (38 non-fatal hemorrhagic strokes) as compared to the placebo group (16 non-fatal hemorrhagic strokes). Patients who entered the trial with a hemorrhagic stroke appeared to be at increased risk for hemorrhagic stroke (16% atorvastatin vs. 4% placebo).

Adverse Reactions from Clinical Studies of Atorvastatin in Pediatric Patients with HeFH

In a 26-week controlled study in pediatric patients with HeFH (ages 10 years to 17 years) (n=140, 31% female; 92% White, 1.6% Black or African American, 1.6% Asian, 4.8% other), the safety and tolerability profile of atorvastatin 10 to 20 mg daily, as an adjunct to diet to reduce total cholesterol, LDL-C, and apo B levels, was generally similar to that of placebo [see Use in Specific Populations (8.4) and Clinical Studies (14.11)].

6.2 Postmarketing Experience

The following adverse reactions have been identified during post-approval use of amlodipine and atorvastatin. Because these reactions are reported voluntarily from a population of uncertain size, it is not always possible to reliably estimate their frequency or establish a causal relationship to drug exposure.

Amlodipine

The following postmarketing event has been reported infrequently where a causal relationship is uncertain: gynecomastia. In postmarketing experience, jaundice and hepatic enzyme elevations (mostly consistent with cholestasis or hepatitis), in some cases severe enough to require hospitalization, have been reported in association with use of amlodipine.

Postmarketing reporting has also revealed a possible association between extrapyramidal disorder and amlodipine.

Amlodipine has been used safely in patients with chronic obstructive pulmonary disease, well-compensated congestive heart failure, coronary artery disease, peripheral vascular disease, diabetes mellitus, and abnormal lipid profiles.

Atorvastatin

Gastrointestinal Disorders: pancreatitis

General Disorders: fatigue

Hepatobiliary Disorders: fatal and non-fatal hepatic failure

Immune System Disorders: anaphylaxis

Injury: tendon rupture

Musculoskeletal and Connective Tissue Disorders: rhabdomyolysis, myositis.

There have been rare reports of immune-mediated necrotizing myopathy associated with statin use.

Nervous System Disorders: dizziness, peripheral neuropathy.

There have been rare reports of cognitive impairment (e.g., memory loss, forgetfulness, amnesia, memory impairment, confusion) associated with the use of all statins. Cognitive impairment was generally nonserious, and reversible upon statin discontinuation, with variable times to symptom onset (1 day to years) and symptom resolution (median of 3 weeks). There have been rare reports of new-onset or exacerbation of myasthenia gravis, including ocular myasthenia, and reports of recurrence when the same or a different statin was administered.

Psychiatric Disorders: depression

Respiratory Disorders: interstitial lung disease

Skin and Subcutaneous Tissue Disorders: angioneurotic edema, bullous rashes (including erythema multiforme, Stevens-Johnson syndrome, and toxic epidermal necrolysis)

7 DRUG INTERACTIONS

Data from a drug-drug interaction study involving 10 mg of amlodipine and 80 mg of atorvastatin in healthy subjects indicate that the pharmacokinetics of amlodipine are not altered when the drugs are co-administered. The effect of amlodipine on the pharmacokinetics of atorvastatin showed no effect on the Cmax: 91% (90% confidence interval: 80 to 103%), but the AUC of atorvastatin increased by 18% (90% confidence interval: 109 to 127%) in the presence of amlodipine, which is not clinically meaningful.

No drug interaction studies have been conducted with CADUET and other drugs, although studies have been conducted in the individual amlodipine and atorvastatin components, as described below:

Amlodipine

7.1 Impact of Other Drugs on Amlodipine

CYP3A Inhibitors

Co-administration with CYP3A inhibitors (moderate and strong) results in increased systemic exposure to amlodipine and may require dose reduction. Monitor for symptoms of hypotension and edema when amlodipine is co-administered with CYP3A inhibitors to determine the need for dose adjustment [see Clinical Pharmacology (12.3)].

CYP3A Inducers

No information is available on the quantitative effects of CYP3A inducers on amlodipine. Blood pressure should be closely monitored when amlodipine is co-administered with CYP3A inducers.

Sildenafil

Monitor for hypotension when sildenafil is co-administered with amlodipine [see Clinical Pharmacology (12.2)].

7.2 Impact of Amlodipine on Other Drugs

Immunosuppressants

Amlodipine may increase the systemic exposure of cyclosporine or tacrolimus when co-administered. Frequent monitoring of trough blood levels of cyclosporine and tacrolimus is recommended and adjust the dose when appropriate [see Clinical Pharmacology (12.3)].

Atorvastatin

7.3 Drug Interactions that may Increase the Risk of Myopathy and Rhabdomyolysis with Atorvastatin

Atorvastatin is a substrate of CYP3A4 and transporters (e.g., OATP1B1/1B3, P-gp, or BCRP). Atorvastatin plasma levels can be significantly increased with concomitant administration of inhibitors of CYP3A4 and transporters. Table 3 includes a list of drugs that may increase exposure to atorvastatin and may increase the risk of myopathy and rhabdomyolysis when used concomitantly and instructions for preventing or managing them [see Warnings and Precautions (5.1) and Clinical Pharmacology (12.3)].

Table 3. Drug Interactions that may Increase the Risk of Myopathy and Rhabdomyolysis with Atorvastatin
Cyclosporine or Gemfibrozil
Clinical Impact: | Atorvastatin plasma levels were significantly increased with concomitant administration of atorvastatin and cyclosporine, an inhibitor of CYP3A4 and OATP1B1 [see Clinical Pharmacology (12.3)]. Gemfibrozil may cause myopathy when given alone. The risk of myopathy and rhabdomyolysis is increased with concomitant use of cyclosporine or gemfibrozil with atorvastatin.
Intervention: | Concomitant use of cyclosporine or gemfibrozil with atorvastatin is not recommended.
Anti-Viral Medications
Clinical Impact: | Atorvastatin plasma levels were significantly increased with concomitant administration of atorvastatin with many anti-viral medications, which are inhibitors of CYP3A4 and/or transporters (e.g., BCRP, OATP1B1/1B3, P-gp, MRP2, and/or OAT2) [see Clinical Pharmacology (12.3)]. Cases of myopathy and rhabdomyolysis have been reported with concomitant use of ledipasvir plus sofosbuvir with atorvastatin.
Intervention: | - Concomitant use of tipranavir plus ritonavir or glecaprevir plus pibrentasvir with atorvastatin is not recommended. - In patients taking lopinavir plus ritonavir, or simeprevir, consider the risk/benefit of concomitant use with atorvastatin. - In patients taking saquinavir plus ritonavir, darunavir plus ritonavir, fosamprenavir, fosamprenavir plus ritonavir, elbasvir plus grazoprevir or letermovir do not exceed atorvastatin 20 mg. - In patients taking nelfinavir, do not exceed atorvastatin 40 mg [see Dosage and Administration (2)]. - Consider the risk/benefit of concomitant use of ledipasvir plus sofosbuvir with atorvastatin. - Monitor all patients for signs and symptoms of myopathy particularly during initiation of therapy and during upward dose titration of either drug.
Examples: | Tipranavir plus ritonavir, glecaprevir plus pibrentasvir, lopinavir plus ritonavir, simeprevir, saquinavir plus ritonavir, darunavir plus ritonavir, fosamprenavir, fosamprenavir plus ritonavir, elbasvir plus grazoprevir, letermovir, nelfinavir, and ledipasvir plus sofosbuvir.
Select Azole Antifungals or Macrolide Antibiotics
Clinical Impact: | Atorvastatin plasma levels were significantly increased with concomitant administration of atorvastatin with select azole antifungals or macrolide antibiotics, due to inhibition of CYP3A4 and/or transporters [see Clinical Pharmacology (12.3)].
Intervention: | In patients taking clarithromycin or itraconazole, do not exceed atorvastatin 20 mg [see Dosage and Administration (2)]. Consider the risk/benefit of concomitant use of other azole antifungals or macrolide antibiotics with atorvastatin. Monitor all patients for signs and symptoms of myopathy particularly during initiation of therapy and during upward dose titration of either drug.
Examples: | Erythromycin, clarithromycin, itraconazole, ketoconazole, posaconazole, and voriconazole.
Niacin
Clinical Impact: | Cases of myopathy and rhabdomyolysis have been observed with concomitant use of lipid modifying dosages of niacin (> 1 gram/day niacin) with atorvastatin.
Intervention: | Consider if the benefit of using lipid modifying dosages of niacin concomitantly with atorvastatin outweighs the increased risk of myopathy and rhabdomyolysis. If concomitant use is decided, monitor patients for signs and symptoms of myopathy particularly during initiation of therapy and during upward dose titration of either drug.
Fibrates (other than Gemfibrozil)
Clinical Impact: | Fibrates may cause myopathy when given alone. The risk of myopathy and rhabdomyolysis is increased with concomitant use of fibrates with atorvastatin.
Intervention: | Consider if the benefit of using fibrates concomitantly with atorvastatin outweighs the increased risk of myopathy and rhabdomyolysis. If concomitant use is decided, monitor patients for signs and symptoms of myopathy particularly during initiation of therapy and during upward dose titration of either drug.
Colchicine
Clinical Impact: | Cases of myopathy and rhabdomyolysis have been reported with concomitant use of colchicine with atorvastatin.
Intervention: | Consider the risk/benefit of concomitant use of colchicine with atorvastatin. If concomitant use is decided, monitor patients for signs and symptoms of myopathy particularly during initiation of therapy and during upward dose titration of either drug.
Grapefruit Juice
Clinical Impact: | Grapefruit juice consumption, especially excessive consumption, more than 1.2 liters/daily can raise the plasma levels of atorvastatin and may increase the risk of myopathy and rhabdomyolysis.
Intervention: | Avoid intake of large quantities of grapefruit juice, more than 1.2 liters daily, when taking atorvastatin.

7.4 Drug Interactions that may Decrease Exposure to Atorvastatin

Table 4 presents drug interactions that may decrease exposure to atorvastatin and instructions for preventing or managing them.

Table 4. Drug Interactions that may Decrease Exposure to Atorvastatin
Rifampin
Clinical Impact: | Concomitant administration of atorvastatin with rifampin, an inducer of cytochrome P450 3A4 and inhibitor of OATP1B1, can lead to variable reductions in plasma concentrations of atorvastatin. Due to the dual interaction mechanism of rifampin, delayed administration of atorvastatin after administration of rifampin has been associated with a significant reduction in atorvastatin plasma concentrations.
Intervention: | Administer atorvastatin and rifampin simultaneously.

7.5 Atorvastatin Effects on Other Drugs

Table 5 presents atorvastatin's effect on other drugs and instructions for preventing or managing them.

Table 5. Atorvastatin Effects on Other Drugs
Oral Contraceptives
Clinical Impact: | Co-administration of atorvastatin and an oral contraceptive increased plasma concentrations of norethindrone and ethinyl estradiol [see Clinical Pharmacology (12.3)].
Intervention: | Consider this when selecting an oral contraceptive for patients taking atorvastatin.
Digoxin
Clinical Impact: | When multiple doses of atorvastatin and digoxin were co-administered, steady state plasma digoxin concentrations increased [see Clinical Pharmacology (12.3)].
Intervention: | Monitor patients taking digoxin appropriately.

8 USE IN SPECIFIC POPULATIONS

8.1 Pregnancy

Risk Summary

Atorvastatin

Discontinue atorvastatin when pregnancy is recognized. Alternatively, consider the ongoing therapeutic needs of the individual patient. Atorvastatin decreases synthesis of cholesterol and possibly other biologically active substances derived from cholesterol; therefore, atorvastatin may cause fetal harm when administered to pregnant patients based on the mechanism of action [see Clinical Pharmacology (12.1)]. In addition, treatment of hyperlipidemia is not generally necessary during pregnancy. Atherosclerosis is a chronic process and the discontinuation of lipid-lowering drugs during pregnancy should have little impact on the outcome of long-term therapy of primary hyperlipidemia for most patients.

Available data from case series and prospective and retrospective observational cohort studies over decades of use with statins in pregnant women have not identified a drug-associated risk of major congenital malformations. Published data from prospective and retrospective observational cohort studies with atorvastatin use in pregnant women are insufficient to determine if there is a drug-associated risk of miscarriage (see Data). In animal reproduction studies, no adverse developmental effects were observed in pregnant rats or rabbits orally administered atorvastatin at doses that resulted in up to 30 and 20 times, respectively, the human exposure at the maximum recommended human dose (MRHD) of 80 mg, based on body surface area (mg/m2). In rats administered atorvastatin during gestation and lactation, decreased postnatal growth and development delay were observed at doses ≥ 6 times the MRHD (see Data).

Amlodipine

The limited available data based on postmarketing reports with amlodipine use in pregnant women are not sufficient to inform a drug-associated risk for major birth defects and miscarriage. There are risks to the mother and fetus associated with poorly controlled hypertension in pregnancy (see Clinical Considerations). In animal reproduction studies, there was no evidence of adverse developmental effects when pregnant rats and rabbits were treated orally with amlodipine maleate during organogenesis at doses approximately 10 and 20-times MRHD, respectively. However for rats, litter size was significantly decreased (by about 50%) and the number of intrauterine deaths was significantly increased (about 5-fold). Amlodipine has been shown to prolong both the gestation period and the duration of labor in rats at this dose (see Data).

The estimated background risk of major birth defects and miscarriage for the indicated population is unknown. All pregnancies have a background risk of birth defect, loss or other adverse outcomes. In the U.S. general population, the estimated background risk of major birth defects and miscarriage in clinically recognized pregnancies is 2 to 4% and 15 to 20%, respectively.

Clinical Considerations

Disease-associated maternal and/or embryo/fetal risk

Hypertension in pregnancy increases the maternal risk for pre-eclampsia, gestational diabetes, premature delivery, and delivery complications (e.g., need for cesarean section and post-partum hemorrhage). Hypertension increases the fetal risk for intrauterine growth restriction and intrauterine death. Pregnant women with hypertension should be carefully monitored and managed accordingly.

Data

Human Data

Atorvastatin

A Medicaid cohort linkage study of 1152 statin-exposed pregnant women compared to 886,996 controls did not find a significant teratogenic effect from maternal use of statins in the first trimester of pregnancy, after adjusting for potential confounders–including maternal age, diabetes mellitus, hypertension, obesity, and alcohol and tobacco use – using propensity score-based methods. The relative risk of congenital malformations between the group with statin use and the group with no statin use in the first trimester was 1.07 (95% confidence interval 0.85 to 1.37) after controlling for confounders, particularly pre-existing diabetes mellitus. There were also no statistically significant increases in any of the organ-specific malformations assessed after accounting for confounders. In the majority of pregnancies, statin treatment was initiated prior to pregnancy and was discontinued at some point in the first trimester when pregnancy was identified. Study limitations include reliance on physician coding to define the presence of a malformation, lack of control for certain confounders such as body mass index, use of prescription dispensing as verification for the use of a statin, and lack of information on non-live births.

Animal Data

Atorvastatin

Was administered to pregnant rats and rabbits during organogenesis at oral doses up to 300 mg/kg/day and 100 mg/kg/day, respectively. Atorvastatin was not teratogenic in rats at doses up to 300 mg/kg/day or in rabbits at doses up to 100 mg/kg/day. These doses resulted in multiples of about 30 times (rat) or 20 times (rabbit) the human exposure at the MRHD based on surface area (mg/m2). In rats, the maternally toxic dose of 300 mg/kg resulted in increased post-implantation loss and decreased fetal body weight. At the maternally toxic doses of 50 and 100 mg/kg/day in rabbits, there was increased post-implantation loss, and at 100 mg/kg/day fetal body weights were decreased.

In a study in pregnant rats administered 20, 100, or 225 mg/kg/day, from gestation day 7 through to lactation day 20 (weaning), there was decreased survival at birth, postnatal day 4, weaning, and post-weaning in pups of mothers dosed with 225 mg/kg/day, a dose at which maternal toxicity was observed. Pup body weight was decreased through postnatal day 21 at 100 mg/kg/day, and through postnatal day 91 at 225 mg/kg/day. Pup development was delayed (rotorod performance at 100 mg/kg/day and acoustic startle at 225 mg/kg/day; pinnae detachment and eye-opening at 225 mg/kg/day). These doses of atorvastatin correspond to 6 times (100 mg/kg) and 22 times (225 mg/kg) the human exposure at the MRHD, based on AUC.

Atorvastatin crosses the rat placenta and reaches a level in fetal liver equivalent to that of maternal plasma.

Amlodipine

No evidence of teratogenicity or other embryo/fetal toxicity was found when pregnant rats and rabbits were treated orally with amlodipine maleate at doses up to 10 mg amlodipine/kg/day (approximately 10 and 20 times the MRHD based on body surface area, respectively) during their respective periods of major organogenesis. However, for rats, litter size was significantly decreased (by about 50%) and the number of intrauterine deaths was significantly increased (about 5-fold) in rats receiving amlodipine maleate at a dose equivalent to 10 mg amlodipine/kg/day for 14 days before mating and throughout mating and gestation. Amlodipine maleate has been shown to prolong both the gestation period and the duration of labor in rats at this dose.

8.2 Lactation

Risk Summary

Atorvastatin

There is no information about the presence of atorvastatin in human milk, the effects of the drug on the breastfed infant or the effects of the drug on milk production. However, it has been shown that another drug in this class passes into human milk. Studies in rats have shown that atorvastatin and/or its metabolites are present in the breast milk of lactating rats. When a drug is present in animal milk, it is likely that the drug will be present in human milk (see Data). Statins, including atorvastatin, decrease cholesterol synthesis and possibly the synthesis of other biologically active substances derived from cholesterol and may cause harm to the breastfed infant.

Because of the potential for serious adverse reactions in a breastfed infant, based on the mechanism of action, advise patients that breastfeeding is not recommended during treatment with CADUET [see Use in Specific Populations (8.1) and Clinical Pharmacology (12.1)].

Data

Following a single oral administration of 10 mg/kg of radioactive atorvastatin to lactating rats, the concentration of total radioactivity was determined. Atorvastatin and/or its metabolites were measured in the breast milk and pup plasma at a 2:1 ratio (milk:plasma).

Amlodipine

Limited available data from a published clinical lactation study reports that amlodipine is present in human milk at an estimated median relative infant dose of 4.2%. No adverse effects of amlodipine on the breastfed infant have been observed. There is no available information on the effects of amlodipine on milk production.

8.4 Pediatric Use

The safety and effectiveness of CADUET have not been established in pediatric populations.

Amlodipine

Amlodipine (2.5 to 5 mg daily) is effective in lowering blood pressure in patients 6 to 17 years [see Clinical Studies (14.1)]. The effect of amlodipine on blood pressure in patients less than 6 years of age is not known.

Atorvastatin

The safety and effectiveness of atorvastatin as an adjunct to diet to reduce LDL-C have been established in pediatric patients 10 years of age and older with HeFH. Use of atorvastatin for this indication is based on a double-blind, placebo-controlled clinical trial in 187 pediatric patients 10 years of age and older with HeFH. In this limited controlled trial, there was no significant effect on growth or sexual maturation in the males or females, or on menstrual cycle length in females.

The safety and effectiveness of atorvastatin as an adjunct to other LDL-C-lowering therapies to reduce LDL-C have been established in pediatric patients 10 years of age and older with HoFH. Use of CADUET for this indication is based on a trial without a concurrent control group in 8 pediatric patients 10 years of age and older with HoFH [see Clinical Studies (14)].

The safety and effectiveness of atorvastatin have not been established in pediatric patients younger than 10 years of age with HeFH or HoFH, or in pediatric patients with other types of hyperlipidemia (other than HeFH or HoFH).

8.5 Geriatric Use

Safety and effectiveness of CADUET have not been established in geriatric populations.

Amlodipine

Clinical studies of amlodipine did not include sufficient numbers of subjects aged 65 and over to determine whether they respond differently from younger subjects. Other reported clinical experience has not identified differences in responses between the elderly and younger patients. In general, dose selection for an elderly patient should be cautious, usually starting at the low end of the dosing range, reflecting the greater frequency of decreased hepatic, renal, or cardiac function, and of concomitant disease or other drug therapy. Elderly patients have decreased clearance of amlodipine with a resulting increase of AUC of approximately 40–60%, and a lower initial dose may be required [see Dosage and Administration (2)].

Atorvastatin

Of the total number of atorvastatin-treated patients in clinical trials, 15813 (40%) were ≥ 65 years old and 2800 (7%) were ≥ 75 years old. No overall differences in safety or effectiveness were observed between these patients and younger patients.

Advanced age (≥65 years) is a risk factor for atorvastatin -associated myopathy and rhabdomyolysis.

Dose selection for an elderly patient should be cautious, recognizing the greater frequency of decreased hepatic, renal, or cardiac function, and of concomitant disease or other drug therapy and the higher risk of myopathy. Monitor geriatric patients receiving CADUET for the increased risk of myopathy [see Warnings and Precautions (5.1) and Clinical Pharmacology (12.3)].

8.6 Renal Impairment

Renal impairment is a risk factor for myopathy and rhabdomyolysis. Monitor all patients with renal impairment for development of myopathy. Renal impairment does not affect the plasma concentrations of atorvastatin, therefore there is no dosage adjustment in patients with renal impairment [see Warnings and Precautions (5.1) and Clinical Pharmacology (12.3)].

8.7 Hepatic Impairment

In patients with chronic alcoholic liver disease, plasma concentrations of atorvastatin are markedly increased. Cmax and AUC are each 4-fold greater in patients with Childs-Pugh A disease. Cmax and AUC are approximately 16-fold and 11-fold increased, respectively, in patients with Childs-Pugh B disease. CADUET is contraindicated in patients with acute liver failure or decompensated cirrhosis [see Contraindications (4)].

10 OVERDOSAGE

There is no information on overdosage with CADUET in humans.

Amlodipine

Overdosage might be expected to cause excessive peripheral vasodilation with marked hypotension and possibly a reflex tachycardia. In humans, experience with intentional overdosage of amlodipine is limited.

Single oral doses of amlodipine maleate equivalent to 40 mg amlodipine/kg and 100 mg amlodipine/kg in mice and rats, respectively, caused deaths. Single oral amlodipine maleate doses equivalent to 4 or more mg amlodipine/kg or higher in dogs (11 or more times the MRHD on a mg/m^2 basis) caused a marked peripheral vasodilation and hypotension.

If overdose should occur with amlodipine, initiate active cardiac and respiratory monitoring. Perform frequent blood pressure measurements. Should hypotension occur, provide cardiovascular support including elevation of the extremities and administration of fluids. If hypotension remains unresponsive to these conservative measures, consider administration of vasopressors (such as phenylephrine) with specific attention to circulating volume and urine output. As amlodipine is highly protein bound, hemodialysis is not likely to be of benefit.

Atorvastatin

No specific antidotes for atorvastatin are known. Contact Poison Control (1-800-222-1222) for latest recommendations. Due to extensive drug binding to plasma proteins, hemodialysis is not expected to significantly enhance atorvastatin clearance.

11 DESCRIPTION

CADUET (amlodipine and atorvastatin) tablets combine the calcium channel blocker amlodipine besylate with the HMG-CoA-reductase inhibitor atorvastatin calcium.

Amlodipine besylate is chemically described as 3-ethyl-5-methyl (±)-2-[(2-aminoethoxy)methyl]-4-(o-chlorophenyl)-1,4-dihydro-6-methyl-3,5-pyridinedicarboxylate, monobenzenesulphonate. Its empirical formula is C20H25ClN2O5∙C6H6O3S.

Atorvastatin calcium is chemically described as [R-(R*, R*)]-2-(4-fluorophenyl)-ß, δ-dihydroxy-5-(1-methylethyl)-3-phenyl-4-[(phenylamino)carbonyl]-1H-pyrrole-1-heptanoic acid, calcium salt (2:1) trihydrate. Its empirical formula is (C33H34FN2O5)2Ca∙3H2O.

The structural formulae for amlodipine besylate and atorvastatin calcium are shown below.

Amlodipine besylate

Atorvastatin calcium

CADUET contains amlodipine besylate, a white to off-white crystalline powder, and atorvastatin calcium, also a white to off-white crystalline powder. Amlodipine besylate has a molecular weight of 567.1 and atorvastatin calcium has a molecular weight of 1209.42. Amlodipine besylate is slightly soluble in water and sparingly soluble in ethanol. Atorvastatin calcium is insoluble in aqueous solutions of pH 4 and below. Atorvastatin calcium is very slightly soluble in distilled water, pH 7.4 phosphate buffer, and acetonitrile; slightly soluble in ethanol; and freely soluble in methanol.

CADUET is available as film-coated tablets containing:

- 5 mg amlodipine equivalent to 6.9 mg amlodipine besylate and 10 mg atorvastatin equivalent to 10.4 mg atorvastatin calcium.
- 5 mg amlodipine equivalent to 6.9 mg amlodipine besylate and 20 mg atorvastatin equivalent to 20.7 mg atorvastatin calcium.
- 5 mg amlodipine equivalent to 6.9 mg amlodipine besylate and 40 mg atorvastatin equivalent to 41.4 mg atorvastatin calcium.
- 5 mg amlodipine equivalent to 6.9 mg amlodipine besylate and 80 mg atorvastatin equivalent to 82.9 mg atorvastatin calcium.
- 10 mg amlodipine equivalent to 13.9 mg amlodipine besylate and 10 mg atorvastatin equivalent to 10.4 mg atorvastatin calcium.
- 10 mg amlodipine equivalent to 13.9 mg amlodipine besylate and 20 mg atorvastatin equivalent to 20.7 mg atorvastatin calcium.
- 10 mg amlodipine equivalent to 13.9 mg amlodipine besylate and 40 mg atorvastatin equivalent to 41.4 mg atorvastatin calcium.
- 10 mg amlodipine equivalent to 13.9 mg amlodipine besylate and 80 mg atorvastatin equivalent to 82.9 mg atorvastatin calcium.

Each film-coated tablet also contains calcium carbonate, croscarmellose sodium, microcrystalline cellulose, pregelatinized starch, polysorbate 80, hydroxypropyl cellulose, purified water, colloidal silicon dioxide (anhydrous), magnesium stearate, Opadry® II White 85F28751 (polyvinyl alcohol, titanium dioxide, PEG 3000, and talc) or Opadry® II Blue 85F10919 (polyvinyl alcohol, titanium dioxide, PEG 3000, talc, and FD&C blue #2).

12 CLINICAL PHARMACOLOGY

12.1 Mechanism of Action

CADUET is a combination of two drugs, a dihydropyridine calcium channel blocker (amlodipine) and an HMG-CoA reductase inhibitor (atorvastatin). The amlodipine component of CADUET inhibits the transmembrane influx of calcium ions into vascular smooth muscle and cardiac muscle. The atorvastatin component of CADUET is a selective, competitive inhibitor of HMG-CoA reductase, the rate-limiting enzyme that converts 3-hydroxy-3-methylglutaryl-coenzyme A to mevalonate, a precursor of sterols, including cholesterol.

Amlodipine

Amlodipine binds to both dihydropyridine and nondihydropyridine binding sites. The contractile processes of cardiac muscle and vascular smooth muscle are dependent upon the movement of extracellular calcium ions into these cells through specific ion channels. Amlodipine inhibits calcium ion influx across cell membranes selectively, with a greater effect on vascular smooth muscle cells than on cardiac muscle cells. Negative inotropic effects can be detected in vitro but such effects have not been seen in intact animals at therapeutic doses. Serum calcium concentration is not affected by amlodipine.

Amlodipine is a peripheral arterial vasodilator that acts directly on vascular smooth muscle to cause a reduction in peripheral vascular resistance and reduction in blood pressure.

The precise mechanisms by which amlodipine relieves angina have not been fully delineated, but are thought to include the following:

Exertional Angina: In patients with exertional angina, amlodipine reduces the total peripheral resistance (afterload) against which the heart works and reduces the rate pressure product, and thus myocardial oxygen demand, at any given level of exercise.

Vasospastic Angina: Amlodipine has been demonstrated to block constriction and restore blood flow in coronary arteries and arterioles in response to calcium, potassium epinephrine, serotonin, and thromboxane A2 analog in experimental animal models and in human coronary vessels in vitro. This inhibition of coronary spasm is responsible for the effectiveness of amlodipine in vasospastic (Prinzmetal's or variant) angina.

Atorvastatin

Atorvastatin is a selective, competitive inhibitor of HMG-CoA reductase, the rate-limiting enzyme that converts 3-hydroxy-3-methylglutaryl-coenzyme A to mevalonate, a precursor of sterols, including cholesterol. In animal models, atorvastatin lowers plasma cholesterol and lipoprotein levels by inhibiting HMG-CoA reductase and cholesterol synthesis in the liver and by increasing the number of hepatic LDL receptors on the cell surface to enhance uptake and catabolism of LDL; atorvastatin also reduces LDL production and the number of LDL particles.

12.2 Pharmacodynamics

Amlodipine

Following administration of therapeutic doses to patients with hypertension, amlodipine produces vasodilation resulting in a reduction of supine and standing blood pressures. These decreases in blood pressure are not accompanied by a significant change in heart rate or plasma catecholamine levels with chronic dosing. Although the acute intravenous administration of amlodipine decreases arterial blood pressure and increases heart rate in hemodynamic studies of patients with chronic stable angina, chronic oral administration of amlodipine in clinical trials did not lead to clinically significant changes in heart rate or blood pressures in normotensive patients with angina.

With chronic once daily oral administration, antihypertensive effectiveness is maintained for at least 24 hours. Plasma concentrations correlate with effect in both young and elderly patients. The magnitude of reduction in blood pressure with amlodipine is also correlated with the height of pretreatment elevation; thus, individuals with moderate hypertension (diastolic pressure 105–114 mmHg) had about a 50% greater response than patients with mild hypertension (diastolic pressure 90–104 mmHg). Normotensive subjects experienced no clinically significant change in blood pressures (+1/–2 mmHg).

In hypertensive patients with normal renal function, therapeutic doses of amlodipine resulted in a decrease in renal vascular resistance and an increase in glomerular filtration rate and effective renal plasma flow without change in filtration fraction or proteinuria.

As with other calcium channel blockers, hemodynamic measurements of cardiac function at rest and during exercise (or pacing) in patients with normal ventricular function treated with amlodipine have generally demonstrated a small increase in cardiac index without significant influence on dP/dt or on left ventricular end diastolic pressure or volume. In hemodynamic studies, amlodipine has not been associated with a negative inotropic effect when administered in the therapeutic dose range to intact animals and man, even when co-administered with beta-blockers to man. Similar findings, however, have been observed in normal or well-compensated patients with heart failure with agents possessing significant negative inotropic effects.

Amlodipine does not change sinoatrial nodal function or atrioventricular conduction in intact animals or man. In patients with chronic stable angina, intravenous administration of 10 mg did not significantly alter A-H and H-V conduction and sinus node recovery time after pacing. Similar results were obtained in patients receiving amlodipine and concomitant beta-blockers. In clinical studies in which amlodipine was administered in combination with beta-blockers to patients with either hypertension or angina, no adverse effects on electrocardiographic parameters were observed. In clinical trials with angina patients alone, amlodipine therapy did not alter electrocardiographic intervals or produce higher degrees of AV blocks.

Atorvastatin

Atorvastatin, as well as some of its metabolites, are pharmacologically active in humans. The liver is the primary site of action and the principal site of cholesterol synthesis and LDL clearance. Drug dosage, rather than systemic drug concentration, correlates better with LDL-C reduction. Individualization of drug dosage should be based on therapeutic response [see Dosage and Administration (2)].

Drug Interactions

Sildenafil: When amlodipine and sildenafil were used in combination, each agent independently exerted its own blood pressure lowering effect [see Drug Interactions (7.1)].

12.3 Pharmacokinetics

Absorption

Amlodipine: After oral administration of therapeutic doses of amlodipine alone, absorption produces peak plasma concentrations between 6 and 12 hours. Absolute bioavailability has been estimated to be between 64% and 90%.

Atorvastatin: After oral administration alone, atorvastatin is rapidly absorbed; maximum plasma concentrations occur within 1 to 2 hours. Extent of absorption increases in proportion to atorvastatin dose. The absolute bioavailability of atorvastatin (parent drug) is approximately 14% and the systemic availability of HMG-CoA reductase inhibitory activity is approximately 30%. The low systemic availability is attributed to presystemic clearance in gastrointestinal mucosa and/or hepatic first-pass metabolism.Although food decreases the rate and extent of drug absorption by approximately 25% and 9%, respectively, as assessed by Cmax and AUC,LDL-C reduction is similar whether atorvastatin is given with or without food Plasma atorvastatin concentrations are lower (approximately 30% for Cmax and AUC) following evening drug administration compared with morning. However, LDL-C reduction is the same regardless of the time of day of drug administration.

CADUET: Following oral administration of CADUET, peak plasma concentrations of amlodipine and atorvastatin are seen at 6 to 12 hours and 1 to 2 hours post dosing, respectively. The rate and extent of absorption (bioavailability) of amlodipine and atorvastatin from CADUET are not significantly different from the bioavailability of amlodipine and atorvastatin administered separately (see above).

The bioavailability of amlodipine from CADUET was not affected by food. Food decreases the rate and extent of absorption of atorvastatin from CADUET by approximately 32% and 11%, respectively, as it does with atorvastatin when given alone. LDL-C reduction is similar whether atorvastatin is given with or without food.

Distribution

Amlodipine: Ex vivo studies have shown that approximately 93% of the circulating amlodipine drug is bound to plasma proteins in hypertensive patients. Steady-state plasma levels of amlodipine are reached after 7 to 8 days of consecutive daily dosing.

Atorvastatin: Mean volume of distribution of atorvastatin is approximately 381 liters. Atorvastatin is ≥98% bound to plasma proteins. A blood/plasma ratio of approximately 0.25 indicates poor drug penetration into red blood cells.

Elimination

Metabolism

Amlodipine: Amlodipine is extensively (about 90%) converted to inactive metabolites via hepatic metabolism.

Atorvastatin: Atorvastatin is extensively metabolized to ortho- and parahydroxylated derivatives and various beta-oxidation products. In vitro inhibition of HMG-CoA reductase by ortho- and parahydroxylated metabolites is equivalent to that of atorvastatin. Approximately 70% of circulating inhibitory activity for HMG-CoA reductase is attributed to active metabolites.

In vitro studies suggest the importance of atorvastatin metabolism by cytochrome P4503A4, consistent with increased plasma concentrations of atorvastatin in humans following co-administration with erythromycin, a known inhibitor of this isozyme [see Drug Interactions (7)]. In animals, the ortho-hydroxy metabolite undergoes further glucuronidation.

Excretion

Amlodipine: Elimination from the plasma is biphasic with a terminal elimination half-life of about 30–50 hours. Ten percent of the parent amlodipine compound and 60% of the metabolites of amlodipine are excreted in the urine.

Atorvastatin: Atorvastatin and its metabolites are eliminated primarily in bile following hepatic and/or extra-hepatic metabolism; however, the drug does not appear to undergo enterohepatic recirculation. Mean plasma elimination half-life of atorvastatin in humans is approximately 14 hours, but the half-life of inhibitory activity for HMG-CoA reductase is 20 to 30 hours because of the contribution of active metabolites. Less than 2% of a dose of atorvastatin is recovered in urine following oral administration.

Specific Populations

Geriatric

Amlodipine: Elderly patients have decreased clearance of amlodipine with a resulting increase in AUC of approximately 40–60%, and a lower initial dose of amlodipine may be required.

Atorvastatin: Plasma concentrations of atorvastatin are higher (approximately 40% for Cmax and 30% for AUC) in healthy elderly subjects (age ≥ 65 years) than in young adults.

Pediatric

Amlodipine: Sixty-two hypertensive patients aged 6 to 17 years received doses of amlodipine between 1.25 mg and 20 mg. Weight-adjusted clearance and volume of distribution were similar to values in adults.

Atorvastatin: Apparent oral clearance of atorvastatin in pediatric subjects appeared similar to that of adults when scaled allometrically by body weight as the body weight was the only significant covariate in atorvastatin population pharmacokinetics model with data including pediatric HeFH patients (ages 10 years to 17 years of age, n=29) in an open-label, 8-week study.

Gender

Atorvastatin: Plasma concentrations of atorvastatin in females differ from those in males (approximately 20% higher for Cmax and 10% lower for AUC); however, there is no clinically significant difference in LDL-C reduction with atorvastatin between males and females.

Renal Impairment

Amlodipine: The pharmacokinetics of amlodipine are not significantly influenced by renal impairment. Patients with renal failure may therefore receive the usual initial amlodipine dose.

Atorvastatin: Renal disease has no influence on the plasma concentrations or LDL-C reduction of atorvastatin [see Use in Specific Populations (8.6)].

While studies have not been conducted in patients with end-stage renal disease, hemodialysis is not expected to clear atorvastatin or amlodipine since both drugs are extensively bound to plasma proteins.

Hepatic Impairment

Amlodipine: Elderly patients and patients with hepatic insufficiency have decreased clearance of amlodipine with a resulting increase in AUC of approximately 40–60%.

Atorvastatin: In patients with chronic alcoholic liver disease, plasma concentrations of atorvastatin are markedly increased. Cmax and AUC are each 4-fold greater in patients with Childs-Pugh A disease. Cmax and AUC of atorvastatin are approximately 16-fold and 11-fold increased, respectively, in patients with Childs-Pugh B disease [see Use in Specific Populations (8.7)].

Heart Failure

Amlodipine: In patients with moderate to severe heart failure, the increase in AUC for amlodipine was similar to that seen in the elderly and in patients with hepatic insufficiency.

Effects of Other Drugs on CADUET

Amlodipine:

Co-administered cimetidine, magnesium-and aluminum hydroxide antacids, sildenafil, and grapefruit juice have no impact on the exposure to amlodipine.

CYP3A inhibitors: Co-administration of a 180 mg daily dose of diltiazem with 5 mg amlodipine in elderly hypertensive patients resulted in a 60% increase in amlodipine systemic exposure. Erythromycin co-administration in healthy volunteers did not significantly change amlodipine systemic exposure. However, strong inhibitors of CYP3A (e.g., itraconazole, clarithromycin) may increase the plasma concentrations of amlodipine to a greater extent [see Drug Interactions (7.1)].

Atorvastatin:

Atorvastatin is a substrate of the hepatic transporters, OATP1B1 and OATP1B3 transporter. Metabolites of atorvastatin are substrates of OATP1B1. Atorvastatin is also identified as a substrate of the efflux transporter BCRP, which may limit the intestinal absorption and biliary clearance of atorvastatin.

Table 6 shows effects of other drugs on the pharmacokinetics of atorvastatin.

Table 6. Effect of Co-administered Drugs on the Pharmacokinetics of Atorvastatin
Co-administered drug and dosage regimen | Atorvastatin
 | Dosage (mg) | Ratio of AUC [Represents ratio of treatments (co-administered drug plus atorvastatin vs atorvastatin alone).] | Ratio of Cmax
[See Sections 5.1 and 7 for clinical significance.] Cyclosporine 5.2 mg/kg/day, stable dose | 10 mg QD [Once daily] for 28 days | 8.69 | 10.66
Tipranavir 500 mg BID [Twice daily] /ritonavir 200 mg BID, 7 days | 10 mg SD [Single dosage] | 9.36 | 8.58
Glecaprevir 400 mg QD/pibrentasvir 120 mg QD, 7 days | 10 mg QD for 7 days | 8.28 | 22.00
Telaprevir 750 mg q8h [Every 8 hours] , 10 days | 20 mg SD | 7.88 | 10.60
, [The dose of saquinavir plus ritonavir in this study is not the clinically used dose. The increase in atorvastatin exposure when used clinically is likely to be higher than what was observed in this study. Therefore, caution should be applied and the lowest dose necessary should be used.] Saquinavir 400 mg BID/ritonavir 400 mg BID, 15 days | 40 mg QD for 4 days | 3.93 | 4.31
Elbasvir 50 mg QD/grazoprevir 200 mg QD, 13 days | 10 mg SD | 1.94 | 4.34
Simeprevir 150 mg QD, 10 days | 40 mg SD | 2.12 | 1.70
Clarithromycin 500 mg BID, 9 days | 80 mg QD for 8 days | 4.54 | 5.38
Darunavir 300 mg BID/ritonavir 100 mg BID, 9 days | 10 mg QD for 4 days | 3.45 | 2.25
Itraconazole 200 mg QD, 4 days | 40 mg SD | 3.32 | 1.20
Letermovir 480 mg QD, 10 days | 20 mg SD | 3.29 | 2.17
Fosamprenavir 700 mg BID/ritonavir 100 mg BID, 14 days | 10 mg QD for 4 days | 2.53 | 2.84
Fosamprenavir 1400 mg BID, 14 days | 10 mg QD for 4 days | 2.30 | 4.04
Nelfinavir 1250 mg BID, 14 days | 10 mg QD for 28 days | 1.74 | 2.22
Grapefruit Juice, 240 mL QD, [Greater increases in AUC (ratio of AUC up to 2.5) and/or Cmax (ratio of Cmax up to 1.71) have been reported with excessive grapefruit consumption (≥ 750 mL – 1.2 liters per day).] | 40 mg SD | 1.37 | 1.16
Diltiazem 240 mg QD, 28 days | 40 mg SD | 1.51 | 1.00
Erythromycin 500 mg QID [Four times daily] , 7 days | 10 mg SD | 1.33 | 1.38
Amlodipine 10 mg, single dose | 80 mg SD | 1.18 | 0.91
Cimetidine 300 mg QID, 2 weeks | 10 mg QD for 2 weeks | 1.00 | 0.89
Colestipol 10 g BID, 24 weeks | 40 mg QD for 8 weeks | NA | 0.74 [Ratio based on a single sample taken 8–16 h post dose.]
Maalox TC® 30 mL QID, 17 days | 10 mg QD for 15 days | 0.66 | 0.67
Efavirenz 600 mg QD, 14 days | 10 mg for 3 days | 0.59 | 1.01
Rifampin 600 mg QD, 7 days (co-administered) [Due to the dual interaction mechanism of rifampin, simultaneous co-administration of atorvastatin with rifampin is recommended, as delayed administration of atorvastatin after administration of rifampin has been associated with a significant reduction in atorvastatin plasma concentrations.] | 40 mg SD | 1.12 | 2.90
Rifampin 600 mg QD, 5 days (doses separated) | 40 mg SD | 0.20 | 0.60
Gemfibrozil 600 mg BID, 7 days | 40 mg SD | 1.35 | 1.00
Fenofibrate 160 mg QD, 7 days | 40 mg SD | 1.03 | 1.02
Boceprevir 800 mg TID [Three times daily] , 7 days | 40 mg SD | 2.32 | 2.66

Effects of CADUET on Other Drugs

Amlodipine:

Amlodipine is a weak inhibitor of CYP3A and may increase exposure to CYP3A substrates.

In vitro data indicate that amlodipine has no effect on the human plasma protein binding of digoxin, phenytoin, warfarin, and indomethacin.

Co-administered amlodipine does not affect the exposure to atorvastatin, digoxin, ethanol and the warfarin prothrombin response time.

Cyclosporine: A prospective study in renal transplant patients (N=11) showed on an average of 40% increase in trough cyclosporine levels when concomitantly treated with amlodipine [see Drug Interactions (7.2)].

Tacrolimus: A prospective study in healthy Chinese volunteers (N=9) with CYP3A5 expressers showed a 2.5- to 4-fold increase in tacrolimus exposure when concomitantly administered with amlodipine compared to tacrolimus alone. This finding was not observed in CYP3A5 non-expressers (N=6). However, a 3-fold increase in plasma exposure to tacrolimus in a renal transplant patient (CYP3A5 non-expresser) upon initiation of amlodipine for the treatment of post-transplant hypertension resulting in reduction of tacrolimus dose has been reported. Irrespective of the CYP3A5 genotype status, the possibility of an interaction cannot be excluded with these drugs [see Drug Interactions (7.2)].

Atorvastatin:

Table 7 shows the effects of atorvastatin on the pharmacokinetics of other drugs.

Table 7. Effect of Atorvastatin on the Pharmacokinetics of Co-administered Drugs
Atorvastatin | Co-administered drug and dosage regimen
 | Drug/Dosage (mg) | Ratio of AUC | Ratio of Cmax
80 mg QD [Once daily] for 15 days | Antipyrine, 600 mg SD [Single dosage] | 1.03 | 0.89
80 mg QD for 10 days | [See Section 7 for clinical significance.] Digoxin 0.25 mg QD, 20 days | 1.15 | 1.20
40 mg QD for 22 days | Oral contraceptive QD, 2 months
40 mg QD for 22 days | – norethindrone 1 mg – ethinyl estradiol 35 µg | 1.28 1.19 | 1.23 1.30
10 mg SD | Tipranavir 500 mg BID [Twice daily] /ritonavir 200 mg BID, 7 days | 1.08 | 0.96
10 mg QD for 4 days | Fosamprenavir 1400 mg BID, 14 days | 0.73 | 0.82
10 mg QD for 4 days | Fosamprenavir 700 mg BID/ritonavir 100 mg BID, 14 days | 0.99 | 0.94

Atorvastatin had no clinically significant effect on prothrombin time when administered to patients receiving chronic warfarin treatment.

13 NONCLINICAL TOXICOLOGY

13.1 Carcinogenesis, Mutagenesis, Impairment of Fertility

Amlodipine

Rats and mice treated with amlodipine maleate in the diet for up to two years, at concentrations calculated to provide daily dosage levels of 0.5, 1.25, and 2.5 mg amlodipine/kg/day, showed no evidence of a carcinogenic effect of the drug. For the mouse, the highest dose was, on a mg/m^2 basis, similar to the MRHD of 10 mg amlodipine/day. [Based on patient weight of 50 kg.] For the rat, the highest dose level was, on a mg/m^2 basis, about twice the MRHD.

Mutagenicity studies conducted with amlodipine maleate revealed no drug related effects at either the gene or chromosome levels.

There was no effect on the fertility of rats treated orally with amlodipine maleate (males for 64 days and females for 14 days prior to mating) at doses up to 10 mg amlodipine/kg/day (8 times the MRHD of 10 mg/day on a mg/m^2 basis).

Atorvastatin

In a 2-year carcinogenicity study with atorvastatin calcium in rats at dose levels equivalent to 10, 30, and 100 mg atorvastatin/kg/day, 2 rare tumors were found in muscle in high-dose females: in one, there was a rhabdomyosarcoma and, in another, there was a fibrosarcoma. This dose represents a plasma AUC (0–24) value of approximately 16 times the mean human plasma drug exposure after an 80 mg oral dose.

A 2-year carcinogenicity study in mice given atorvastatin calcium at dose levels equivalent to 100, 200, or 400 mg atorvastatin/kg/day resulted in a significant increase in liver adenomas in high-dose males and liver carcinomas in high-dose females. These findings occurred at plasma AUC (0–24) values of approximately 6 times the mean human plasma drug exposure after an 80 mg oral dose.

In vitro, atorvastatin was not mutagenic or clastogenic in the following tests with and without metabolic activation: the Ames test with Salmonella typhimurium and Escherichia coli, the HGPRT forward mutation assay in Chinese hamster lung cells, and the chromosomal aberration assay in Chinese hamster lung cells. Atorvastatin was negative in the in vivo mouse micronucleus test.

In female rats, atorvastatin at doses up to 225 mg/kg (56 times the human exposure) did not cause adverse effects on fertility. Studies in male rats performed at doses up to 175 mg/kg (15 times the human exposure) produced no changes in fertility. There was aplasia and aspermia in the epididymis of 2 of 10 rats treated with atorvastatin calcium at a dose equivalent to 100 mg atorvastatin/kg/day for 3 months (16 times the human AUC at the 80 mg dose); testis weights were significantly lower at 30 and 100 mg/kg/day and epididymal weight was lower at 100 mg/kg/day. Male rats given the equivalent of 100 mg atorvastatin/kg/day for 11 weeks prior to mating had decreased sperm motility, spermatid head concentration, and increased abnormal sperm. Atorvastatin caused no adverse effects on semen parameters, or reproductive organ histopathology in dogs given doses of atorvastatin calcium equivalent to 10, 40, or 120 mg atorvastatin/kg/day for 2 years.

14 CLINICAL STUDIES

14.1 Amlodipine for Hypertension

Adult Patients

The antihypertensive efficacy of amlodipine has been demonstrated in a total of 15 double-blind, placebo-controlled, randomized studies involving 800 patients on amlodipine and 538 on placebo. Once daily administration produced statistically significant placebo-corrected reductions in supine and standing blood pressures at 24 hours postdose, averaging about 12/6 mmHg in the standing position and 13/7 mmHg in the supine position in patients with mild to moderate hypertension. Maintenance of the blood pressure effect over the 24-hour dosing interval was observed, with little difference in peak and trough effect. Tolerance was not demonstrated in patients studied for up to 1 year. The 3 parallel, fixed dose, dose response studies showed that the reduction in supine and standing blood pressures was dose related within the recommended dosing range. Effects on diastolic pressure were similar in young and older patients. The effect on systolic pressure was greater in older patients, perhaps because of greater baseline systolic pressure. Effects were similar in black patients and in white patients.

Pediatric Patients

Two hundred sixty-eight hypertensive patients aged 6 to 17 years were randomized first to amlodipine 2.5 or 5 mg once daily for 4 weeks and then randomized again to the same dose or to placebo for another 4 weeks. Patients receiving 2.5 mg or 5 mg at the end of 8 weeks had significantly lower systolic blood pressure than those secondarily randomized to placebo. The magnitude of the treatment effect is difficult to interpret, but it is probably less than 5 mmHg systolic on the 5 mg dose and 3.3 mmHg systolic on the 2.5 mg dose. Adverse events were similar to those seen in adults.

14.2 Amlodipine for Chronic Stable Angina

The effectiveness of 5–10 mg/day of amlodipine in exercise-induced angina has been evaluated in 8 placebo-controlled, double-blind clinical trials of up to 6 weeks duration involving 1038 patients (684 amlodipine, 354 placebo) with chronic stable angina. In 5 of the 8 studies, significant increases in exercise time (bicycle or treadmill) were seen with the 10 mg dose. Increases in symptom-limited exercise time averaged 12.8% (63 sec) for amlodipine 10 mg, and averaged 7.9% (38 sec) for amlodipine 5 mg. Amlodipine 10 mg also increased time to 1 mm ST segment deviation in several studies and decreased angina attack rate. The sustained efficacy of amlodipine in angina patients has been demonstrated over long-term dosing. In patients with angina, there were no clinically significant reductions in blood pressures (4/1 mmHg) or changes in heart rate (+0.3 bpm).

14.3 Amlodipine for Vasospastic Angina

In a double-blind, placebo-controlled clinical trial of 4 weeks duration in 50 patients, amlodipine therapy decreased attacks by approximately 4/week compared with a placebo decrease of approximately 1/week (p < 0.01). Two of 23 amlodipine and 7 of 27 placebo patients discontinued from the study for lack of clinical improvement.

14.4 Amlodipine for Coronary Artery Disease

In PREVENT, 825 patients with angiographically documented CAD were randomized to amlodipine (5–10 mg once daily) or placebo and followed for 3 years. Although the study did not show significance on the primary objective of change in coronary luminal diameter as assessed by quantitative coronary angiography, the data suggested a favorable outcome with respect to fewer hospitalizations for angina and revascularization procedures in patients with CAD.

CAMELOT enrolled 1318 patients with CAD recently documented by angiography, without left main coronary disease and without heart failure or an ejection fraction < 40%. Patients (76% males, 89% Caucasian, 93% enrolled at U.S. sites, 89% with a history of angina, 52% without PCI, 4% with PCI and no stent, and 44% with a stent) were randomized to double-blind treatment with either amlodipine (5–10 mg once daily) or placebo in addition to standard care that included aspirin (89%), statins (83%), beta-blockers (74%), nitroglycerin (50%), anticoagulants (40%), and diuretics (32%), but excluded other calcium channel blockers. The mean duration of follow-up was 19 months. The primary endpoint was the time to first occurrence of one of the following events: hospitalization for angina pectoris, coronary revascularization, myocardial infarction, cardiovascular death, resuscitated cardiac arrest, hospitalization for heart failure, stroke/TIA, or peripheral vascular disease. A total of 110 (16.6%) and 151 (23.1%) first events occurred in the amlodipine and placebo groups, respectively, for a hazard ratio of 0.691 (95% CI: 0.540–0.884, p=0.003). The primary endpoint is summarized in Figure 1 below. The outcome of this study was largely derived from the prevention of hospitalizations for angina and the prevention of revascularization procedures (see Table 8). Effects in various subgroups are shown in Figure 2.

In an angiographic substudy (n=274) conducted within CAMELOT, there was no significant difference between amlodipine and placebo on the change of atheroma volume in the coronary artery as assessed by intravascular ultrasound.

Figure 1. Kaplan-Meier Analysis of Composite Clinical Outcomes for Amlodipine versus Placebo

Figure 2. Effects on Primary Endpoint of Amlodipine versus Placebo across Sub-Groups

Table 8 below summarizes the significant composite endpoint and clinical outcomes from the composites of the primary endpoint. The other components of the primary endpoint including cardiovascular death, resuscitated cardiac arrest, myocardial infarction, hospitalization for heart failure, stroke/TIA, or peripheral vascular disease did not demonstrate a significant difference between amlodipine and placebo.

Table 8. Incidence of Significant Clinical Outcomes for CAMELOT
Clinical Outcomes N (%) | Amlodipine (N=663) | Placebo (N=655) | Risk Reduction (p-value)
Composite CV Endpoint | 110 (16.6) | 151 (23.1) | 31% (0.003)
Hospitalization for Angina [Total patients with these events.] | 51 (7.7) | 84 (12.8) | 42% (0.002)
Coronary Revascularization | 78 (11.8) | 103 (15.7) | 27% (0.033)

14.5 Amlodipine for Heart Failure

Amlodipine has been compared to placebo in four 8–12 week studies of patients with NYHA Class II/III heart failure, involving a total of 697 patients. In these studies, there was no evidence of worsened heart failure based on measures of exercise tolerance, NYHA classification, symptoms, or left ventricular ejection fraction. In a long-term (follow-up at least 6 months, mean 13.8 months) placebo-controlled mortality/morbidity study of amlodipine 5–10 mg in 1153 patients with NYHA Classes III (n=931) or IV (n=222) heart failure on stable doses of diuretics, digoxin, and ACE inhibitors, amlodipine had no effect on the primary endpoint of the study which was the combined endpoint of all-cause mortality and cardiac morbidity (as defined by life-threatening arrhythmia, acute myocardial infarction, or hospitalization for worsened heart failure), or on NYHA classification, or symptoms of heart failure. Total combined all-cause mortality and cardiac morbidity events were 222/571 (39%) for patients on amlodipine and 246/583 (42%) for patients on placebo; the cardiac morbid events represented about 25% of the endpoints in the study.

Another study (PRAISE-2) randomized patients with NYHA Class III (80%) or IV (20%) heart failure without clinical symptoms or objective evidence of underlying ischemic disease, on stable doses of ACE inhibitors (99%), digitalis (99%), and diuretics (99%), to placebo (n=827) or amlodipine (n=827) and followed them for a mean of 33 months. There was no statistically significant difference between amlodipine and placebo in the primary endpoint of all-cause mortality (95% confidence limits from 8% reduction to 29% increase on amlodipine). With amlodipine there were more reports of pulmonary edema.

14.6 Atorvastatin for Prevention of Cardiovascular Disease

In the Anglo-Scandinavian Cardiac Outcomes Trial (ASCOT), the effect of atorvastatin on fatal and non-fatal coronary heart disease was assessed in 10,305 patients with hypertension, 40-80 years of age (mean of 63 years; 19% female; 95% White, 3% Black or African American, 1% South Asian, 1% other), without a previous myocardial infarction and with total cholesterol (TC) levels ≤ 251 mg/dL. Additionally, all patients had at least 3 of the following cardiovascular risk factors: male gender (81%), age > 55 years (85%), smoking (33%), diabetes (24%), history of CHD in a first-degree relative (26%), TC:HDL > 6 (14%), peripheral vascular disease (5%), left ventricular hypertrophy (14%), prior cerebrovascular event (10%), specific ECG abnormality (14%), proteinuria/albuminuria (62%). In this double-blind, placebo-controlled trial, patients were treated with antihypertensive therapy (goal BP < 140/90 mm Hg for patients without diabetes; < 130/80 mm Hg for patients with diabetes) and allocated to either atorvastatin 10 mg daily (n=5168) or placebo (n=5137), using a covariate adaptive method which took into account the distribution of nine baseline characteristics of patients already enrolled and minimized the imbalance of those characteristics across the groups. Patients were followed for a median duration of 3.3 years.

The effect of 10 mg/day of atorvastatin on lipid levels was similar to that seen in previous clinical trials.

Atorvastatin significantly reduced the rate of coronary events [either fatal coronary heart disease (46 events in the placebo group vs. 40 events in the atorvastatin group) or non-fatal MI (108 events in the placebo group vs. 60 events in the atorvastatin group)] with a relative risk reduction of 36% [(based on incidences of 1.9% for atorvastatin vs. 3.0% for placebo), p=0.0005 (see Figure 3)]. The risk reduction was consistent regardless of age, smoking status, obesity, or presence of renal dysfunction. The effect of atorvastatin was seen regardless of baseline LDL levels.

Figure 3. Effect of Atorvastatin 10 mg/day on Cumulative Incidence of Non-Fatal Myocardial Infarction or Coronary Heart Disease Death (in ASCOT-LLA)

Atorvastatin also significantly decreased the relative risk for revascularization procedures by 42% (incidences of 1.4% for atorvastatin and 2.5% for placebo). Although the reduction of fatal and non-fatal strokes did not reach a pre-defined significance level (p=0.01), a favorable trend was observed with a 26% relative risk reduction (incidences of 1.7% for atorvastatin and 2.3% for placebo). There was no significant difference between the treatment groups for death due to cardiovascular causes (p=0.51) or noncardiovascular causes (p=0.17).

In the Collaborative Atorvastatin Diabetes Study (CARDS), the effect of atorvastatin on cardiovascular disease (CVD) endpoints was assessed in 2838 subjects (94% White, 2% Black or African American, 2% South Asian, 1% other, 68% male), ages 40–75 with type 2 diabetes based on WHO criteria, without prior history of cardiovascular disease and with LDL ≤ 160 mg/dL and triglycerides (TG) ≤ 600 mg/dL. In addition to diabetes, subjects had 1 or more of the following risk factors: current smoking (23%), hypertension (80%), retinopathy (30%), or microalbuminuria (9%) or macroalbuminuria (3%). No subjects on hemodialysis were enrolled in the trial. In this multicenter, placebo-controlled, double-blind clinical trial, subjects were randomly allocated to either atorvastatin 10 mg daily (1429) or placebo (1411) in a 1:1 ratio and were followed for a median duration of 3.9 years. The primary endpoint was the occurrence of any of the major cardiovascular events: myocardial infarction, acute CHD death, unstable angina, coronary revascularization, or stroke. The primary analysis was the time to first occurrence of the primary endpoint.

Baseline characteristics of subjects were: mean age of 62 years; mean HbA1c 7.7%; median LDL-C 120 mg/dL; median TC 207 mg/dL; median TG 151 mg/dL; median HDL-C 52 mg/dL.

The effect of atorvastatin 10 mg/day on lipid levels was similar to that seen in previous clinical trials.

Atorvastatin significantly reduced the rate of major cardiovascular events (primary endpoint events) (83 events in the atorvastatin group vs. 127 events in the placebo group) with a relative risk reduction of 37%, HR 0.63, 95% CI (0.48, 0.83) (p=0.001) (see Figure 4). An effect of atorvastatin was seen regardless of age, sex, or baseline lipid levels.

Atorvastatin significantly reduced the risk of stroke by 48% (21 events in the atorvastatin group vs. 39 events in the placebo group), HR 0.52, 95% CI (0.31, 0.89) (p=0.016) and reduced the risk of MI by 42% (38 events in the atorvastatin group vs. 64 events in the placebo group), HR 0.58, 95.1% CI (0.39, 0.86) (p=0.007). There was no significant difference between the treatment groups for angina, revascularization procedures, and acute CHD death.

There were 61 deaths in the atorvastatin group vs. 82 deaths in the placebo group (HR 0.73, p=0.059).

Figure 4. Effect of Atorvastatin 10 mg/day on Time to Occurrence of Major Cardiovascular Event (myocardial infarction, acute CHD death, unstable angina, coronary revascularization, or stroke) in CARDS

In the Treating to New Targets Study (TNT), the effect of atorvastatin 80 mg/day vs. atorvastatin 10 mg/day on the reduction in cardiovascular events was assessed in 10,001 subjects (94% White, 81% male, 38% ≥ 65 years) with clinically evident coronary heart disease who had achieved a target LDL-C level < 130 mg/dL after completing an 8-week, open-label, run-in period with atorvastatin 10 mg/day. Subjects were randomly assigned to either 10 mg/day or 80 mg/day of atorvastatin and followed for a median duration of 4.9 years. The primary endpoint was the time to first occurrence of any of the following major cardiovascular events (MCVE): death due to CHD, non-fatal myocardial infarction, resuscitated cardiac arrest, and fatal and non-fatal stroke. The mean LDL-C, TC, TG, non-HDL, and HDL cholesterol ‎ levels at 12 weeks were 73, 145, 128, 98, and 47 mg/dL during treatment with 80 mg of atorvastatin and 99, 177, 152, 129, and 48 mg/dL during treatment with 10 mg of atorvastatin.

Treatment with atorvastatin 80 mg/day significantly reduced the rate of MCVE (434 events in the 80 mg/day group vs. 548 events in the 10 mg/day group) with a relative risk reduction of 22%, HR 0.78, 95% CI (0.69, 0.89), p=0.0002 (see Figure 5 and Table 9).

The overall risk reduction was consistent regardless of age (< 65, ≥ 65) or sex.

Figure 5. Effect of Atorvastatin 80 mg/day vs. 10 mg/day on Time to Occurrence of Major Cardiovascular Events (TNT)

Table 9. Overview of Efficacy Results in TNT
Endpoint | Atorvastatin; 10 mg; (N=5006) |  | Atorvastatin; 80 mg; (N=4995) |  | HR [Atorvastatin 80 mg: atorvastatin 10 mg] (95% CI)
PRIMARY ENDPOINT | n | (%) | n | (%)
First major cardiovascular endpoint | 548 | (10.9) | 434 | (8.7) | 0.78 (0.69, 0.89)
Components of the Primary Endpoint
CHD death | 127 | (2.5) | 101 | (2.0) | 0.80 (0.61, 1.03)
Non-fatal, non-procedure related MI | 308 | (6.2) | 243 | (4.9) | 0.78 (0.66, 0.93)
Resuscitated cardiac arrest | 26 | (0.5) | 25 | (0.5) | 0.96 (0.56, 1.67)
Stroke (fatal and non-fatal) | 155 | (3.1) | 117 | (2.3) | 0.75 (0.59, 0.96)
SECONDARY ENDPOINTS [Secondary endpoints not included in primary endpoint. HR=hazard ratio; CHD=coronary heart disease; CI=confidence interval; MI=myocardial infarction; CHF=congestive heart failure; CV=cardiovascular; PVD=peripheral vascular disease; CABG=coronary artery bypass graft]
First CHF with hospitalization | 164 | (3.3) | 122 | (2.4) | 0.74 (0.59, 0.94)
First PVD endpoint | 282 | (5.6) | 275 | (5.5) | 0.97 (0.83, 1.15)
First CABG or other coronary revascularization procedure [Component of other secondary endpoints] | 904 | (18.1) | 667 | (13.4) | 0.72 (0.65, 0.80)
First documented angina endpoint | 615 | (12.3) | 545 | (10.9) | 0.88 (0.79, 0.99)
All-cause mortality | 282 | (5.6) | 284 | (5.7) | 1.01 (0.85, 1.19)
Components of All-Cause Mortality
Cardiovascular death | 155 | (3.1) | 126 | (2.5) | 0.81 (0.64, 1.03)
Noncardiovascular death | 127 | (2.5) | 158 | (3.2) | 1.25 (0.99, 1.57)
Cancer death | 75 | (1.5) | 85 | (1.7) | 1.13 (0.83, 1.55)
Other non-CV death | 43 | (0.9) | 58 | (1.2) | 1.35 (0.91, 2.00)
Suicide, homicide, and other traumatic non-CV death | 9 | (0.2) | 15 | (0.3) | 1.67 (0.73, 3.82)

Of the events that comprised the primary efficacy endpoint, treatment with atorvastatin 80 mg/day significantly reduced the rate of non-fatal, non-procedure related MI and fatal and non-fatal stroke, but not CHD death or resuscitated cardiac arrest (Table 9). Of the predefined secondary endpoints, treatment with atorvastatin 80 mg/day significantly reduced the rate of coronary revascularization, angina, and hospitalization for heart failure, but not peripheral vascular disease. The reduction in the rate of CHF with hospitalization was only observed in the 8% of patients with a prior history of CHF.

There was no significant difference between the treatment groups for all-cause mortality (Table 9). The proportions of subjects who experienced cardiovascular death, including the components of CHD death and fatal stroke, were numerically smaller in the atorvastatin 80 mg group than in the atorvastatin 10 mg treatment group. The proportions of subjects who experienced noncardiovascular death were numerically larger in the atorvastatin 80 mg group than in the atorvastatin 10 mg treatment group.

14.7 Atorvastatin for Primary Hyperlipidemia in Adults

Atorvastatin reduces total-C, LDL-C, apo B, and TG, and increases HDL-C in patients with hyperlipidemia (heterozygous familial and nonfamilial) and mixed dyslipidemia. Therapeutic response is seen within 2 weeks, and maximum response is usually achieved within 4 weeks and maintained during chronic therapy.

In two multicenter, placebo-controlled, dose-response trials in patients with hyperlipidemia, atorvastatin given as a single dose over 6 weeks significantly reduced total-C, LDL-C, apo B, and TG. (Pooled results are provided in Table 10).

Table 10. Dose Response in Patients with Primary Hyperlipidemia (Adjusted Mean % Change From Baseline)a

Dose | N | TC | LDL-C | Apo B | TG | HDL-C
Placebo | 21 | 4 | 4 | 3 | 10 | -3
10 | 22 | -29 | -39 | -32 | -19 | 6
20 | 20 | -33 | -43 | -35 | -26 | 9
40 | 21 | -37 | -50 | -42 | -29 | 6
80 | 23 | -45 | -60 | -50 | -37 | 5

a Results are pooled from 2 dose-response trials.

In three multicenter, double-blind trials in patients with hyperlipidemia, atorvastatin was compared to other statins. After randomization, patients were treated for 16 weeks with either atorvastatin 10 mg per day or a fixed dose of the comparative agent (Table 11).

Table 11. Mean Percentage Change from Baseline at Endpoint (Double-Blind, Randomized, Active-Controlled Trials)
Treatment (Daily Dosage) | N | Total-C | LDL-C | Apo B | TG | HDL-C | HDL-C
Trial 1
Atorvastatin 10 mg | 707 | -27 | -36 [A negative value for the 95% CI for the difference between treatments favors atorvastatin for all except HDL C, for which a positive value favors atorvastatin. If the range does not include 0, this indicates a statistically significant difference.] | -28 | -17 | +7 | -37
Lovastatin 20 mg | 191 | -19 | -27 | -20 | -6 | +7 | -28
95% CI for Diff |  | -9.2, -6.5 | -10.7, -7.1 | -10.0, -6.5 | -15.2, -7.1 | -1.7, 2.0 | -11.1, -7.1
Trial 2
Atorvastatin 10 mg | 222 | -25 [Significantly different from pravastatin, ANCOVA, p ≤ 0.05] | -35 | -27 | -17 | +6 | -36
Pravastatin 20 mg | 77 | -17 | -23 | -17 | -9 | +8 | -28
95% CI for Diff [Significantly different from lovastatin, ANCOVA, p ≤ 0.05] |  | -10.8, -6.1 | -14.5, -8.2 | -13.4, -7.4 | -14.1, -0.7 | -4.9, 1.6 | -11.5, -4.1
Trial 3
Atorvastatin 10 mg | 132 | -29 [Significantly different from simvastatin, ANCOVA, p ≤ 0.05] | -37 | -34 | -23 | +7 | -39
Simvastatin 10 mg | 45 | -24 | -30 | -30 | -15 | +7 | -33
95% CI for Diff |  | -8.7, -2.7 | -10.1, -2.6 | -8.0, -1.1 | -15.1, -0.7 | -4.3, 3.9 | -9.6, -1.9

Table 11 does not contain data comparing the effects of atorvastatin 10 mg and higher dosage of lovastatin, pravastatin, and simvastatin. The drugs compared in the trials summarized in the table are not necessarily exchangeable.

14.8 Atorvastatin for Hypertriglyceridemia in Adults

The response to atorvastatin in 64 patients with isolated hypertriglyceridemia treated across several clinical trials is shown in the table below (Table 12). For the atorvastatin-treated patients, median (min, max) baseline TG level was 565 (267–1,502).

Table 12. Combined Patients with Isolated Elevated TG: Median (min, max) Percentage Change From Baseline
 | Placebo (N=12) | Atorvastatin 10 mg (N=37) | Atorvastatin 20 mg (N=13) | Atorvastatin 80 mg (N=14)
Triglycerides | -12.4 (-36.6, 82.7) | -41.0 (-76.2, 49.4) | -38.7 (-62.7, 29.5) | -51.8 (-82.8, 41.3)
Total-C | -2.3 (-15.5, 24.4) | -28.2 (-44.9, -6.8) | -34.9 (-49.6, -15.2) | -44.4 (-63.5, -3.8)
LDL-C | 3.6 (-31.3, 31.6) | -26.5 (-57.7, 9.8) | -30.4 (-53.9, 0.3) | -40.5 (-60.6, -13.8)
HDL-C | 3.8 (-18.6, 13.4) | 13.8 (-9.7, 61.5) | 11.0 (-3.2, 25.2) | 7.5 (-10.8, 37.2)
non-HDL-C | -2.8 (-17.6, 30.0) | -33.0 (-52.1, -13.3) | -42.7 (-53.7, -17.4) | -51.5 (-72.9, -4.3)

14.9 Atorvastatin for Dysbetalipoproteinemia in Adults

The results of an open-label crossover trial of 16 patients (genotypes: 14 apo E2/E2 and 2 apo E3/E2) with dysbetalipoproteinemia are shown in the table below (Table 13).

Table 13. Open-Label Crossover Trial of 16 Patients with Dysbetalipoproteinemia (Fredrickson Type III)

 |  | Median % Change (min, max)
 | Median (min, max) at Baseline (mg/dL) | Atorvastatin 10 mg | Atorvastatin 80 mg
Total-C | 442 (225, 1320) | -37 (-85, 17) | -58 (-90, -31)
Triglycerides | 678 (273, 5990) | -39 (-92, -8) | -53 (-95, -30)
Intermediate-density lipoprotein cholesterol (IDL-C) + VLDL-C | 215 (111, 613) | -32 (-76, 9) | -63 (-90, -8)
non-HDL-C | 411 (218, 1272) | -43 (-87, -19) | -64 (-92, -36)

14.10 Atorvastatin for Homozygous Familial Hypercholesterolemia in Adults and Pediatric Patients

In a trial without a concurrent control group, 29 patients (mean age of 22 years, median age of 24 years, 31% < 18 years) with HoFH received maximum daily doses of 20 to 80 mg of atorvastatin. The mean LDL-C reduction in this trial was 18%. Twenty-five patients with a reduction in LDL-C had a mean response of 20% (range of 7% to 53%, median of 24%); the remaining 4 patients had 7% to 24% increases in LDL-C. Five of the 29 patients had absent LDL-receptor function. Of these, 2 patients also had a portacaval shunt and had no significant reduction in LDL-C. The remaining 3 receptor-negative patients had a mean LDL-C reduction of 22%.

14.11 Atorvastatin for Heterozygous Familial Hypercholesterolemia in Pediatric Patients

In a double-blind, placebo-controlled trial followed by an open-label phase, 187 males and post-menarchal females 10 years to 17 years of age (mean age 14.1 years; 31% female; 92% White, 1.6% Black or African American, 1.6% Asian, 4.8% other) with HeFH or severe hypercholesterolemia, were randomized to atorvastatin (n=140) or placebo (n=47) for 26 weeks and then all received atorvastatin for 26 weeks. Inclusion in the trial required 1) a baseline LDL-C level ≥ 190 mg/dL or 2) a baseline LDL-C level ≥ 160 mg/dL and positive family history of FH or documented premature cardiovascular disease in a first or second-degree relative. The mean baseline LDL-C value was 219 mg/dL (range: 139-385 mg/dL) in the atorvastatin group compared to 230 mg/dL (range: 160-325 mg/dL) in the placebo group. The dosage of atorvastatin (once daily) was 10 mg for the first 4 weeks and uptitrated to 20 mg if the LDL-C level was > 130 mg/dL. The number of atorvastatin-treated patients who required uptitration to 20 mg after Week 4 during the double-blind phase was 78 (56%). Atorvastatin significantly decreased plasma levels of total-C, LDL-C, triglycerides, and apolipoprotein B during the 26-week double-blind phase (see Table 14).

Table 14. Lipid-Altering Effects of Atorvastatin in Adolescent Males and Females with Heterozygous Familial Hypercholesterolemia or Severe Hypercholesterolemia (Mean Percentage Change from Baseline at Endpoint in Intention-to-Treat Population)

DOSAGE | N | Total-C | LDL-C | HDL-C | TG | Apo B
Placebo | 47 | -1.5 | -0.4 | -1.9 | 1.0 | 0.7
Atorvastatin | 140 | -31.4 | -39.6 | 2.8 | -12.0 | -34.0

The mean achieved LDL-C value was 130.7 mg/dL (range: 70–242 mg/dL) in the atorvastatin group compared to 228.5 mg/dL (range: 152–385 mg/dL) in the placebo group during the 26-week double-blind phase.

Atorvastatin was also studied in a three year open-label, uncontrolled trial that included 163 patients with HeFH who were 10 years to 15 years old (82 males and 81 females). All patients had a clinical diagnosis of HeFH confirmed by genetic analysis (if not already confirmed by family history). Approximately 98% were White, and less than 1% were Black, African American or Asian. Mean LDL-C at baseline was 232 mg/dL. The starting atorvastatin dosage was 10 mg once daily and doses were adjusted to achieve a target of <130 mg/dL LDL-C. The reductions in LDL-C from baseline were generally consistent across age groups within the trial as well as with previous clinical trials in both adult and pediatric placebo-controlled trials.

14.12 CADUET for Hypertension and Dyslipidemia

In a double-blind, placebo-controlled study, a total of 1660 patients with co-morbid hypertension and dyslipidemia received once daily treatment with eight dose combinations of amlodipine and atorvastatin (5/10, 10/10, 5/20, 10/20, 5/40, 10/40, 5/80, or 10/80 mg), amlodipine alone (5 mg or 10 mg), atorvastatin alone (10 mg, 20 mg, 40 mg, or 80 mg), or placebo. In addition to concomitant hypertension and dyslipidemia, 15% of the patients had diabetes mellitus, 22% were smokers, and 14% had a positive family history of cardiovascular disease. At eight weeks, all eight combination-treatment groups of amlodipine and atorvastatin demonstrated statistically significant dose-related reductions in systolic blood pressure (SBP), diastolic blood pressure (DBP), and LDL-C compared to placebo, with no overall modification of effect of either component on SBP, DBP, and LDL-C (Table 15).

Table 15. Effects of Amlodipine and Atorvastatin on Blood Pressure and LDL-C

BP (mmHg) | Atorvastatin
Amlodipine | 0 mg | 10 mg | 20 mg | 40 mg | 80 mg
0 mg | — | -1.5/-0.8 | -3.2/-0.6 | -3.2/-1.8 | -3.4/-0.8
5 mg | -9.8/-4.3 | -10.7/-4.9 | -12.3/-6.1 | -9.7/-4.0 | -9.2/-5.1
10 mg | -13.2/-7.1 | -12.9/-5.8 | -13.1/-7.3 | -13.3/-6.5 | -14.6/-7.8
LDL-C (% change) | Atorvastatin
Amlodipine | 0 mg | 10 mg | 20 mg | 40 mg | 80 mg
0 mg | — | -32.3 | -38.4 | -42.0 | -46.1
5 mg | 1.0 | -37.6 | -41.2 | -43.8 | -47.3
10 mg | -1.4 | -35.5 | -37.5 | -42.1 | -48.0

16 HOW SUPPLIED/STORAGE AND HANDLING

CADUET® tablets contain amlodipine besylate and atorvastatin calcium equivalent to amlodipine and atorvastatin in the dose strengths described below.

CADUET tablets are differentiated by tablet color/size and are engraved with a unique number on one side. Combinations of atorvastatin with 5 mg amlodipine are oval and film-coated white tablets and combinations of atorvastatin with 10 mg amlodipine are oval and are film-coated blue tablets. CADUET tablets are supplied for oral administration in the following strengths and package configurations:

Table 16. CADUET Packaging Configurations
CADUET
Package Configuration | Tablet Strength mg (amlodipine / atorvastatin) | NDC # | Engraving Side 1 / Side 2 | Tablet Color | Tablet Shape
Bottle of 30 | 5/10 | 0069-2150-30 or 0069-6180-30 | CDT 051/Pfizer | White | Oval
Bottle of 30 | 5/20 | 0069-2170-30 or 0069-6323-30 | CDT 052/Pfizer | White | Oval
Bottle of 30 | 5/40 | 0069-2190-30 or 0069-6565-30 | CDT 054/Pfizer | White | Oval
Bottle of 30 | 5/80 | 0069-2260-30 or 0069-6747-30 | CDT 058/Pfizer | White | Oval
Bottle of 30 | 10/10 | 0069-2160-30 or 0069-7810-30 | CDT 101/Pfizer | Blue | Oval
Bottle of 30 | 10/20 | 0069-2180-30 or 0069-7232-30 | CDT 102/Pfizer | Blue | Oval
Bottle of 30 | 10/40 | 0069-2250-30 or 0069-7654-30 | CDT 104/Pfizer | Blue | Oval
Bottle of 30 | 10/80 | 0069-2270-30 or 0069-7476-30 | CDT 108/Pfizer | Blue | Oval

STORAGE AND HANDLING

Store at 25°C (77°F); excursions permitted to 15°C -30°C (59°F -86°F) [see USP Controlled Room Temperature].

17 PATIENT COUNSELING INFORMATION

Advise the patient to read the FDA-approved patient labeling (Patient Information).

Myopathy and Rhabdomyolysis

Advise patients that CADUET may cause myopathy and rhabdomyolysis. Inform patients that the risk is also increased when taking certain types of medication or consuming large quantities of grapefruit juice and they should discuss all medication, both prescription and over the counter, with their healthcare provider. Instruct patients to promptly report any unexplained muscle pain, tenderness or weakness particularly if accompanied by malaise or fever [see Warnings and Precautions (5.1), Drug Interactions (7.1)].

Hepatic Dysfunction

Inform patients that CADUET may cause liver enzyme elevations and possibly liver failure. Advise patients to promptly report fatigue, anorexia, right upper abdominal discomfort, dark urine, or jaundice [see Warnings and Precautions (5.3)].

Increases in HbA1c and Fasting Serum Glucose Levels

Inform patients that increases in HbA1c and fasting serum glucose levels may occur with CADUET. Encourage patients to optimize lifestyle measures, including regular exercise, maintaining a healthy body weight, and making healthy food choices [see Warnings and Precautions (5.6)].

Pregnancy

Advise pregnant patients and patients who can become pregnant of the potential risk to a fetus. Advise patients to inform their healthcare provider of a known or suspected pregnancy to discuss if CADUET should be discontinued [see Use in Specific Populations (8.1)].

Lactation

Advise patients that breastfeeding is not recommended during treatment with CADUET [see Use in Specific Populations (8.2)].

This product's labeling may have been updated. For the most recent prescribing information, please visit www.pfizer.com.

LAB-0276-44.0

PATIENT INFORMATION

CADUET® (CAD-oo-et)
(amlodipine and atorvastatin)
Tablets

Read the patient information that comes with CADUET before you start taking it, and each time you get a refill. There may be new information. This information does not replace talking with your healthcare provider about your condition or treatment. If you have any questions about CADUET, ask your healthcare provider or pharmacist.

What is CADUET?

CADUET is a prescription drug that combines Norvasc® (amlodipine besylate) and Lipitor® (atorvastatin calcium) in one pill.

CADUET is used in adults who need both Norvasc and Lipitor.

Norvasc is used to treat:

- High blood pressure (hypertension) and
- Chest pain (angina) and
- Blocked arteries of the heart (coronary artery disease)

Lipitor is used to lower the levels of "bad" cholesterol and triglycerides in your blood. It can also raise the levels of "good" cholesterol.

Lipitor is also used to lower the risk for heart attack, stroke, certain types of heart surgery, and chest pain in patients who have heart disease or risk factors for heart disease such as:

- age, smoking, high blood pressure, low levels of "good" cholesterol, heart disease in the family.

Lipitor can lower the risk for heart attack or stroke in patients with diabetes and risk factors such as:

- diabetic eye or kidney problems, smoking, or high blood pressure.

CADUET has not been studied in children.

Who should not use CADUET?

Do not use CADUET if you:

- Have liver problems (acute liver failure or decompensated cirrhosis).
- Are allergic to anything in CADUET. The active ingredients are atorvastatin calcium and amlodipine besylate. Stop using CADUET and get medical help right away if you have symptoms of a serious allergic reaction including:
- swelling of your face, lips, tongue or throat
- problems breathing or swallowing
- fainting or feeling dizzy
- very rapid heartbeat
- severe skin rash or itching
- flu-like symptoms including fever, sore throat, cough, tiredness, and joint pain

See the end of this leaflet for a complete list of ingredients.

What should I tell my healthcare provider before taking CADUET?

Tell your healthcare provider about all of your health conditions, including, if you:

- have unexplained muscle aches or weakness
- drink more than 2 glasses of alcohol daily
- have heart disease
- have diabetes
- have thyroid problems
- have kidney problems
- had a stroke
- are pregnant or plan to become pregnant. CADUET may harm your unborn baby. If you become pregnant, stop taking CADUET and call your healthcare provider right away.
- are breastfeeding or plan to breastfeed. You and your healthcare provider should decide if you will take CADUET or breastfeed. You should not do both. Talk to your healthcare provider about the best way to feed your baby if you take CADUET.

Tell your healthcare provider about all the medicines you take, including prescription and over-the-counter medicines, vitamins, and herbal supplements. CADUET and certain other medicines can increase the risk of muscle problems or other side effects. Especially tell your healthcare provider if you take medicines for:

- your immune system (cyclosporine)
- cholesterol (gemfibrozil)
- infections (erythromycin, clarithromycin, itraconazole, ketoconazole, posaconazole, and
- voriconazole)
- birth control pills
- heart failure (digoxin)
- gout (colchicine)
- niacin
- fibrates
- treating HIV, AIDS, or hepatitis C (anti-virals)

- tipranavir plus ritonavir

- glecaprevir plus pibrentasvir

- ledipasvir plus sofosbuvir

- simeprevir

- saquinavir plus ritonavir

- darunavir plus ritonavir

- fosamprenavir

- fosamprenavir plus ritonavir

- elbasvir plus grazoprevir

- letermovir

- nelfinavir

You can use nitroglycerin and CADUET together. If you take nitroglycerin for chest pain (angina), do not stop taking it while taking CADUET.

Ask your healthcare provider or pharmacist for a list of medicines if you are not sure. Know all the medicines you take. Keep a list of them with you to show your healthcare provider and pharmacist when you get a new medicine.

How should I take CADUET?

- Take CADUET exactly as your healthcare provider tells you to take it.
- Do not change your dose or stop CADUET without talking to your healthcare provider.
- Your healthcare provider may do blood tests to check your cholesterol levels during your treatment with CADUET. Your dose of CADUET may be changed based on these blood test results.
- Take CADUET each day at any time of day. CADUET can be taken with or without food.
- Do not break the tablets before taking them. Talk to your healthcare provider if you have a problem swallowing pills.
- Your healthcare provider may start you on a cholesterol-lowering diet before giving you CADUET. Stay on this low-fat diet when you take CADUET.
- If you miss a dose, take it as soon as you remember. Do not take CADUET if it has been more than 12 hours since you missed your last dose. Wait and take the next dose at your regular time. Do not take 2 doses of CADUET at the same time. If you take too much CADUET or overdose, call your healthcare provider or Poison Control Center at 1-800-222-1222 or go to the nearest emergency room right away.

What should I avoid while taking CADUET?

- Avoid drinking more than 1.2 liters of grapefruit juice each day.

What are possible side effects of CADUET?

CADUET can cause serious side effects including:

- Muscle pain, tenderness and weakness (myopathy). Muscle problems, including muscle breakdown, can be serious in some people and, rarely, cause kidney damage that can lead to death.
Tell your healthcare provider right away if you have:
- unexplained muscle pain, tenderness, or weakness, especially if you also have a fever or feel more tired than usual while you take CADUET.
- muscle problems that do not go away after your healthcare provider has told you to stop taking CADUET. Your healthcare provider may do further tests to diagnose the cause of your muscle problems.
Your chances of getting muscle problems are higher if you:
- are taking certain other medicines while you take CADUET
- drink large amounts of grapefruit juice
- are 65 years of age or older
- have thyroid problems (hypothyroidism) that are not controlled
- have kidney problems
- are taking higher doses of CADUET
- Liver problems. Your healthcare provider should do blood tests to check your liver before you start taking CADUET and if you have symptoms of liver problems while you take CADUET. Call your healthcare provider right away if you have the following symptoms of liver problems:
- feel tired or weak
- nausea or vomiting
- loss of appetite
- upper belly pain
- dark amber colored urine
- yellowing of your skin or the whites of your eyes
- Low blood pressure or dizziness
- Muscle rigidity, tremor and/or abnormal muscle movement
- Increase in blood sugar level. Your blood sugar level may increase while you are taking CADUET.

Exercise regularly and make healthy food choices to maintain healthy body weight.

Call your healthcare provider right away if:
2. allergic reactions including swelling of the face, lips, tongue, and/or throat that may cause difficulty in breathing or swallowing which may require treatment right away
3. you have allergic skin reactions
4. Chest pain that does not go away or gets worse. Sometimes when you start CADUET or increase your dose, chest pain can get worse or a heart attack can happen. If this happens, call your healthcare provider or go to the emergency room right away.

Common side effects of CADUET include:

- nasal congestion, sore throat, runny nose

- muscle and joint pain

- diarrhea

- pain in extremity

- urinary tract infection

- upset stomach

- nausea

- musculoskeletal pain

- muscle spasms

- trouble sleeping

- throat pain

- swelling of your legs or ankles

Additional side effects have been reported: tiredness, tendon problems, memory loss, and confusion.

Talk to your healthcare provider or pharmacist about side effects that bother you or do not go away.

There are other side effects of CADUET. Ask your healthcare provider or pharmacist for a complete list.

How do I store CADUET?

- Store CADUET at room temperature, 68°F to 77°F (20°C to 25°C).
- Do not keep medicine that is out-of-date or that you no longer need.
- Keep CADUET and all medicines out of the reach of children.

General information about the safe and effective use of CADUET

Medicines are sometimes prescribed for purposes other than those listed in a Patient Information leaflet. Do not use CADUET for a condition for which it was not prescribed. Do not give CADUET to other people, even if they have the same symptoms that you have. It may harm them.

If you want more information about CADUET, talk with your healthcare provider. You can ask your pharmacist or healthcare provider for information about CADUET that is written for health professionals.

What is high blood pressure (hypertension)?

You have high blood pressure when the force of blood against the walls of your arteries stays high. This can damage your heart and other parts of your body. Drugs that lower blood pressure lower your risk of having a stroke or heart attack.

What is angina (chest pain)?

Angina is a pain that keeps coming back when part of your heart does not get enough blood. It feels like something is pressing or squeezing your chest under the breastbone. Sometimes you can feel it in your shoulders, arms, neck, jaw, or back.

What is cholesterol?

Cholesterol is a fat-like substance made in your body. It is also found in foods. You need some cholesterol for good health, but too much is not good for you. Cholesterol can clog your blood vessels.

What is a heart attack?

A heart attack occurs when heart muscle does not get enough blood. Symptoms include chest pain, trouble breathing, nausea, and weakness. Heart muscle cells may be damaged or die. The heart cannot pump well or may stop beating.

What is a stroke?

A stroke occurs when nerve cells in the brain do not get enough blood. The cells may be damaged or die. The damaged cells may cause weakness or problems speaking or thinking.

WHAT ARE THE INGREDIENTS IN CADUET?

Active ingredients: amlodipine besylate, atorvastatin calcium

Inactive ingredients: calcium carbonate, croscarmellose sodium, microcrystalline cellulose, pregelatinized starch, polysorbate 80, hydroxypropyl cellulose, purified water, colloidal silicon dioxide (anhydrous), magnesium stearate

Film coating: Opadry® II White 85F28751 (polyvinyl alcohol, titanium dioxide, PEG 3000, and talc) or Opadry® II Blue 85F10919 (polyvinyl alcohol, titanium dioxide, PEG 3000, talc, and FD&C blue #2)

LAB-0347-15.0
Revised November 2024

PACKAGE LABEL

PRINCIPAL DISPLAY PANEL - 5 mg/10 mg Tablet Bottle Label

Pfizer
NDC 0069-2150-30

Caduet®

(amlodipine besylate/
atorvastatin calcium)

Tablets

5 mg/10 mg*

30 Tablets
Rx only

PACKAGE LABEL

PRINCIPAL DISPLAY PANEL - 5 mg/20 mg Tablet Bottle Label

Pfizer
NDC 0069-2170-30

Caduet®

(amlodipine besylate/
atorvastatin calcium)

Tablets

5 mg/20 mg*

30 Tablets
Rx only

PACKAGE LABEL

PRINCIPAL DISPLAY PANEL - 5 mg/40 mg Tablet Bottle Label

Pfizer
NDC 0069-2190-30

Caduet®

(amlodipine besylate/
atorvastatin calcium)

Tablets

5 mg/40 mg*

30 Tablets
Rx only

PACKAGE LABEL

PRINCIPAL DISPLAY PANEL - 5 mg/80 mg Tablet Bottle Label

Pfizer
NDC 0069-2260-30

Caduet®

(amlodipine besylate/
atorvastatin calcium)

Tablets

5 mg/80 mg*

30 Tablets
Rx only

PACKAGE LABEL

PRINCIPAL DISPLAY PANEL - 10 mg/10 mg Tablet Bottle Label

Pfizer
NDC 0069-2160-30

Caduet®

(amlodipine besylate/
atorvastatin calcium)

Tablets

10 mg/10 mg*

30 Tablets
Rx only

PACKAGE LABEL

PRINCIPAL DISPLAY PANEL - 10 mg/20 mg Tablet Bottle Label

Pfizer
NDC 0069-2180-30

Caduet®

(amlodipine besylate/
atorvastatin calcium)

Tablets

10 mg/20 mg*

30 Tablets
Rx only

PACKAGE LABEL

PRINCIPAL DISPLAY PANEL - 10 mg/40 mg Tablet Bottle Label

Pfizer
NDC 0069-2250-30

Caduet®

(amlodipine besylate/
atorvastatin calcium)

Tablets

10 mg/40 mg*

30 Tablets
Rx only

PACKAGE LABEL

PRINCIPAL DISPLAY PANEL - 10 mg/80 mg Tablet Bottle Label

Pfizer
NDC 0069-2270-30

Caduet®

(amlodipine besylate/
atorvastatin calcium)

Tablets

10 mg/80 mg*

30 Tablets
Rx only

PRINCIPAL DISPLAY PANEL - 5 mg/10 mg Tablet Bottle Label - 6180-30

Pfizer
NDC 0069-6180-30

Caduet®
(amlodipine and
atorvastatin)
tablets

5 mg/10 mg*

30 Tablets
Rx only

PRINCIPAL DISPLAY PANEL - 5 mg/20 mg Tablet Bottle Label - 6323-30

Pfizer
NDC 0069-6323-30

Caduet®
(amlodipine and
atorvastatin)
tablets

5 mg/20 mg*

30 Tablets
Rx only

PRINCIPAL DISPLAY PANEL - 5 mg/40 mg Tablet Bottle Label - 6565-30

Pfizer
NDC 0069-6565-30

Caduet®
(amlodipine and
atorvastatin)
tablets

5 mg/40 mg*

30 Tablets
Rx only

PRINCIPAL DISPLAY PANEL - 5 mg/80 mg Tablet Bottle Label - 6747-30

Pfizer
NDC 0069-6747-30

Caduet®
(amlodipine and
atorvastatin)
tablets

5 mg/80 mg*

30 Tablets
Rx only

PRINCIPAL DISPLAY PANEL - 10 mg/10 mg Tablet Bottle Label - 7810-30

Pfizer
NDC 0069-7810-30

Caduet®
(amlodipine and
atorvastatin)
tablets

10 mg/10 mg*

30 Tablets
Rx only

PRINCIPAL DISPLAY PANEL - 10 mg/20 mg Tablet Bottle Label - 7232-30

Pfizer
NDC 0069-7232-30

Caduet®
(amlodipine and
atorvastatin)
tablets

10 mg/20 mg*

30 Tablets
Rx only

PRINCIPAL DISPLAY PANEL - 10 mg/40 mg Tablet Bottle Label - 7654-30

Pfizer
NDC 0069-7654-30

Caduet®
(amlodipine and
atorvastatin)
tablets

10 mg/40 mg*

30 Tablets
Rx only

PRINCIPAL DISPLAY PANEL - 10 mg/80 mg Tablet Bottle Label - 7476-30

Pfizer
NDC 0069-7476-30

Caduet®
(amlodipine and
atorvastatin)
tablets

10 mg/80 mg*

30 Tablets
Rx only